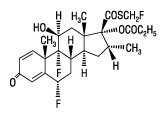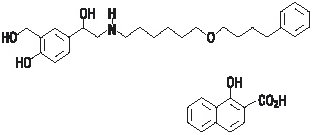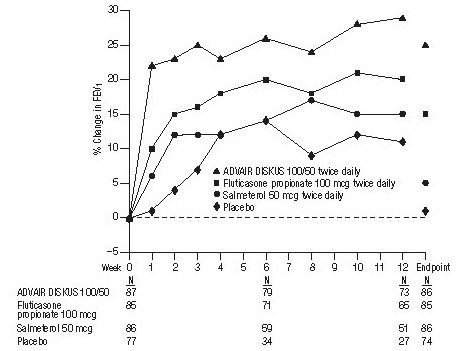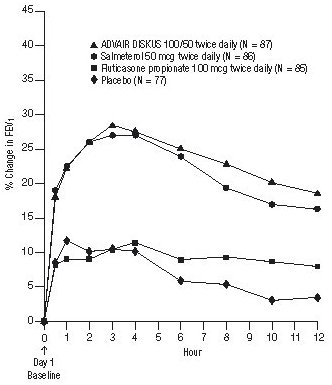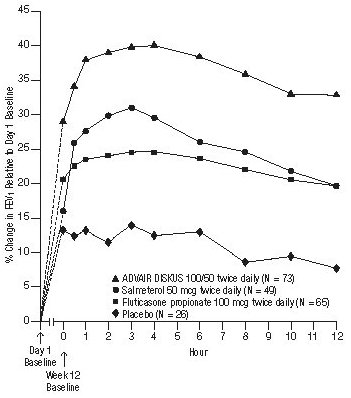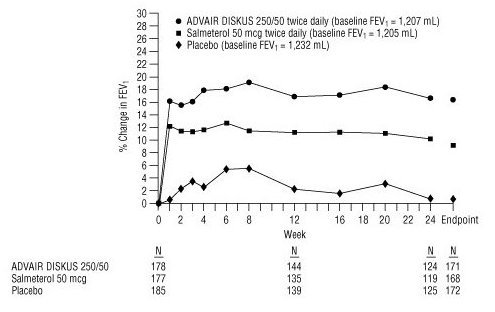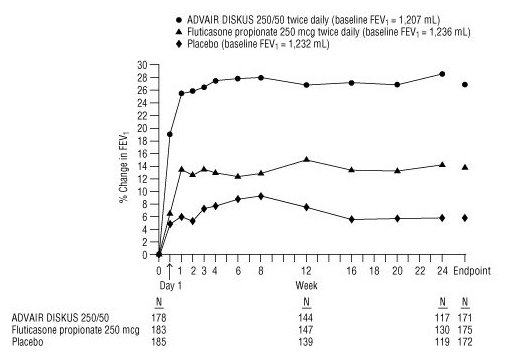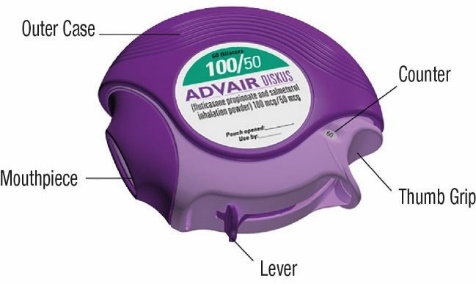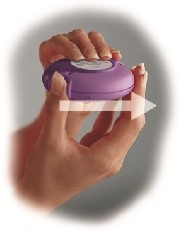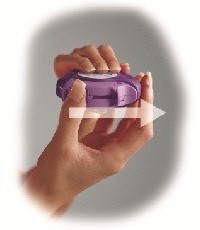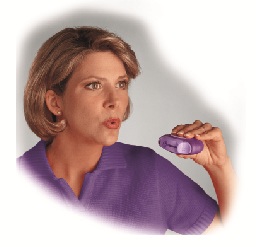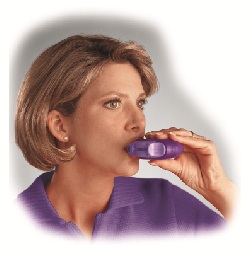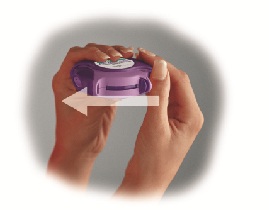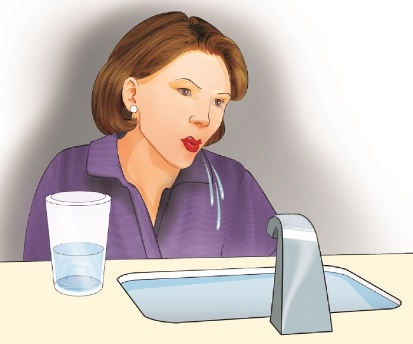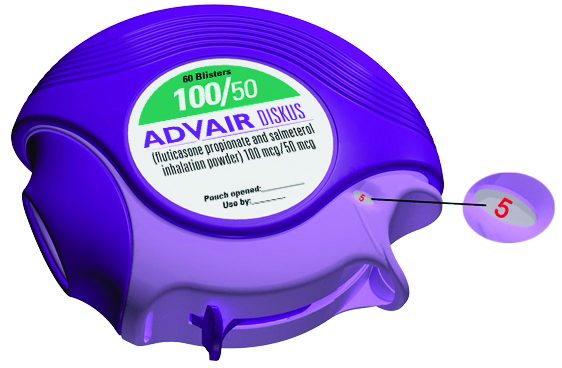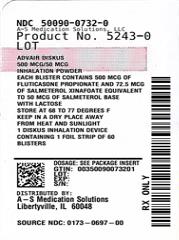 DRUG LABEL: ADVAIR
NDC: 50090-0732 | Form: POWDER
Manufacturer: A-S Medication Solutions
Category: prescription | Type: HUMAN PRESCRIPTION DRUG LABEL
Date: 20251029

ACTIVE INGREDIENTS: SALMETEROL XINAFOATE 50 ug/1 1; FLUTICASONE PROPIONATE 500 ug/1 1
INACTIVE INGREDIENTS: LACTOSE

HIGHLIGHTS OF PRESCRIBING INFORMATION

These highlights do not include all the information needed to use ADVAIR DISKUS safely and effectively. See full prescribing information for ADVAIR DISKUS.
ADVAIR DISKUS (fluticasone propionate and salmeterol inhalation powder), for oral inhalation use
Initial U.S. Approval: 2000

1 INDICATIONS AND USAGE

ADVAIR DISKUS is a combination product containing a corticosteroid and a long-acting beta2-adrenergic agonist (LABA) indicated for:

- Twice-daily treatment of asthma in patients aged 4 years and older. (1.1)
- Maintenance treatment of airflow obstruction and reducing exacerbations in patients with chronic obstructive pulmonary disease (COPD). (1.2)

Important limitation of use: Not indicated for relief of acute bronchospasm. (1.1, 1.2)

2 DOSAGE AND ADMINISTRATION

- For oral inhalation only. (2)
- Treatment of asthma in patients aged 12 years and older: 1 inhalation of ADVAIR DISKUS 100/50, ADVAIR DISKUS 250/50, or ADVAIR DISKUS 500/50 twice daily. Starting dosage is based on asthma severity. (2.1)
- Treatment of asthma in patients aged 4 to 11 years: 1 inhalation of ADVAIR DISKUS 100/50 twice daily. (2.1)
- Maintenance treatment of COPD: 1 inhalation of ADVAIR DISKUS 250/50 twice daily. (2.2)

3 DOSAGE FORMS AND STRENGTHS

Inhalation powder: Inhaler containing a combination of fluticasone propionate (100, 250, or 500 mcg) and salmeterol (50 mcg) as a powder formulation for oral inhalation. (3)

4 CONTRAINDICATIONS

- Primary treatment of status asthmaticus or acute episodes of asthma or COPD requiring intensive measures. (4)
- Severe hypersensitivity to milk proteins or demonstrated hypersensitivity to fluticasone propionate, salmeterol, or any of the excipients. (4)

5 WARNINGS AND PRECAUTIONS

- LABA monotherapy increases the risk of serious asthma-related events. (5.1)
- Do not initiate in acutely deteriorating asthma or COPD. Do not use to treat acute symptoms. (5.2)
- Do not use in combination with an additional medicine containing a LABA because of risk of overdose. (5.3)
- Candida albicans infection of the mouth and pharynx may occur. Monitor patients periodically. Advise the patient to rinse his/her mouth with water without swallowing after inhalation to help reduce the risk. (5.4)
- Increased risk of pneumonia in patients with COPD. Monitor patients for signs and symptoms of pneumonia. (5.5)
- Potential worsening of infections (e.g., existing tuberculosis; fungal, bacterial, viral, or parasitic infections; ocular herpes simplex). Use with caution in patients with these infections. More serious or even fatal course of chickenpox or measles can occur in susceptible patients. (5.6)
- Risk of impaired adrenal function when transferring from systemic corticosteroids. Taper patients slowly from systemic corticosteroids if transferring to ADVAIR DISKUS. (5.7)
- Hypercorticism and adrenal suppression may occur with very high dosages or at the regular dosage in susceptible individuals. If such changes occur, discontinue ADVAIR DISKUS slowly. (5.8)
- If paradoxical bronchospasm occurs, discontinue ADVAIR DISKUS and institute alternative therapy. (5.10)
- Use with caution in patients with cardiovascular or central nervous system disorders because of beta-adrenergic stimulation. (5.12)
- Assess for decrease in bone mineral density initially and periodically thereafter. (5.13)
- Monitor growth of pediatric patients. (5.14)
- Glaucoma and cataracts may occur with long-term use of inhaled corticosteroids. Consider referral to an ophthalmologist in patients who develop ocular symptoms or use ADVAIR DISKUS long term. (5.15)
- Be alert to eosinophilic conditions, hypokalemia, and hyperglycemia. (5.16, 5.18)
- Use with caution in patients with convulsive disorders, thyrotoxicosis, diabetes mellitus, and ketoacidosis. (5.17)

6 ADVERSE REACTIONS

Most common adverse reactions (incidence ≥3%) include:

- Asthma: Upper respiratory tract infection or inflammation, pharyngitis, dysphonia, oral candidiasis, bronchitis, cough, headaches, nausea and vomiting. (6.1)
- COPD: Pneumonia, oral candidiasis, throat irritation, dysphonia, viral respiratory infections, headaches, musculoskeletal pain. (6.2)

To report SUSPECTED ADVERSE REACTIONS, contact GlaxoSmithKline at 1-888-825-5249 or FDA at 1-800-FDA-1088 or www.fda.gov/medwatch.

7 DRUG INTERACTIONS

- Strong cytochrome P450 3A4 inhibitors (e.g., ritonavir, ketoconazole): Use not recommended. May increase risk of systemic corticosteroid and cardiovascular effects. (7.1)
- Monoamine oxidase inhibitors and tricyclic antidepressants: Use with extreme caution. May potentiate effect of salmeterol on vascular system. (7.2)
- Beta-blockers: Use with caution. May block bronchodilatory effects of beta-agonists and produce severe bronchospasm. (7.3)
- Diuretics: Use with caution. Electrocardiographic changes and/or hypokalemia associated with non–potassium-sparing diuretics may worsen with concomitant beta-agonists. (7.4)

8 USE IN SPECIFIC POPULATIONS

Hepatic impairment: Monitor patients for signs of increased drug exposure. (8.6)

FULL PRESCRIBING INFORMATION

1 INDICATIONS AND USAGE

1.1 Treatment of Asthma

ADVAIR DISKUS is indicated for the twice-daily treatment of asthma in patients aged 4 years and older. ADVAIR DISKUS should be used for patients not adequately controlled on a long-term asthma control medication such as an inhaled corticosteroid (ICS) or whose disease warrants initiation of treatment with both an ICS and long-acting beta2-adrenergic agonist (LABA).

Important Limitation of Use

ADVAIR DISKUS is NOT indicated for the relief of acute bronchospasm.

1.2 Maintenance Treatment of Chronic Obstructive Pulmonary Disease

ADVAIR DISKUS 250/50 is indicated for the twice-daily maintenance treatment of airflow obstruction in patients with chronic obstructive pulmonary disease (COPD), including chronic bronchitis and/or emphysema. ADVAIR DISKUS 250/50 is also indicated to reduce exacerbations of COPD in patients with a history of exacerbations. ADVAIR DISKUS 250/50 twice daily is the only approved dosage for the treatment of COPD because an efficacy advantage of the higher strength ADVAIR DISKUS 500/50 over ADVAIR DISKUS 250/50 has not been demonstrated.

Important Limitation of Use

ADVAIR DISKUS is NOT indicated for the relief of acute bronchospasm.

2 DOSAGE AND ADMINISTRATION

ADVAIR DISKUS should be administered as 1 inhalation twice daily by the orally inhaled route only. After inhalation, the patient should rinse his/her mouth with water without swallowing to help reduce the risk of oropharyngeal candidiasis.

More frequent administration or a greater number of inhalations (more than 1 inhalation twice daily) of the prescribed strength of ADVAIR DISKUS is not recommended as some patients are more likely to experience adverse effects with higher doses of salmeterol. Patients using ADVAIR DISKUS should not use additional LABA for any reason. [See Warnings and Precautions (5.3, 5.12).]

2.1 Asthma

If asthma symptoms arise in the period between doses, an inhaled, short-acting beta2-agonist should be taken for immediate relief.

Adult and Adolescent Patients Aged 12 Years and Older

For patients aged 12 years and older, the dosage is 1 inhalation twice daily, approximately 12 hours apart.

When choosing the starting dosage strength of ADVAIR DISKUS, consider the patients’ disease severity, based on their previous asthma therapy, including the ICS dosage, as well as the patients’ current control of asthma symptoms and risk of future exacerbation.

The maximum recommended dosage is ADVAIR DISKUS 500/50 twice daily.

Improvement in asthma control following inhaled administration of ADVAIR DISKUS can occur within 30 minutes of beginning treatment, although maximum benefit may not be achieved for 1 week or longer after starting treatment. Individual patients will experience a variable time to onset and degree of symptom relief.

For patients who do not respond adequately to the starting dosage after 2 weeks of therapy, replacing the current strength of ADVAIR DISKUS with a higher strength may provide additional improvement in asthma control.

If a previously effective dosage regimen fails to provide adequate improvement in asthma control, the therapeutic regimen should be reevaluated and additional therapeutic options (e.g., replacing the current strength of ADVAIR DISKUS with a higher strength, adding additional ICS, initiating oral corticosteroids) should be considered.

Pediatric Patients Aged 4 to 11 Years

For patients with asthma aged 4 to 11 years who are not controlled on an ICS, the dosage is 1 inhalation of ADVAIR DISKUS 100/50 twice daily, approximately 12 hours apart.

2.2 Chronic Obstructive Pulmonary Disease

The recommended dosage for patients with COPD is 1 inhalation of ADVAIR DISKUS 250/50 twice daily, approximately 12 hours apart.

If shortness of breath occurs in the period between doses, an inhaled, short-acting beta2-agonist should be taken for immediate relief.

3 DOSAGE FORMS AND STRENGTHS

Inhalation powder: Inhaler containing a foil blister strip of powder formulation for oral inhalation. The strip contains a combination of fluticasone propionate 100, 250, or 500 mcg and salmeterol 50 mcg per blister.

4 CONTRAINDICATIONS

The use of ADVAIR DISKUS is contraindicated in the following conditions:

- Primary treatment of status asthmaticus or other acute episodes of asthma or COPD where intensive measures are required [see Warnings and Precautions (5.2)].
- Severe hypersensitivity to milk proteins or demonstrated hypersensitivity to fluticasone propionate, salmeterol, or any of the excipients [see Warnings and Precautions (5.11), Adverse Reactions (6.3), Description (11)].

5 WARNINGS AND PRECAUTIONS

5.1 Serious Asthma-Related Events – Hospitalizations, Intubations, Death

Use of LABA as monotherapy (without ICS) for asthma is associated with an increased risk of asthma-related death [see Salmeterol Multicenter Asthma Research Trial (SMART)]. Available data from controlled clinical trials also suggest that use of LABA as monotherapy increases the risk of asthma-related hospitalization in pediatric and adolescent patients. These findings are considered a class effect of LABA monotherapy. When LABA are used in fixed-dose combination with ICS, data from large clinical trials do not show a significant increase in the risk of serious asthma-related events (hospitalizations, intubations, death) compared with ICS alone (see Serious Asthma-Related Events with Inhaled Corticosteroid/Long-acting Beta2-adrenergic Agonists).

Serious Asthma-Related Events with Inhaled Corticosteroid/Long-acting Beta2-adrenergic Agonists

Four (4) large, 26-week, randomized, double-blind, active-controlled clinical safety trials were conducted to evaluate the risk of serious asthma-related events when LABA were used in fixed-dose combination with ICS compared with ICS alone in subjects with asthma. Three (3) trials included adult and adolescent subjects aged 12 years and older: 1 trial compared fluticasone propionate/salmeterol inhalation powder (ADVAIR DISKUS) with fluticasone propionate inhalation powder [see Clinical Studies (14.1)], 1 trial compared mometasone furoate/formoterol with mometasone furoate, and 1 trial compared budesonide/formoterol with budesonide. The fourth trial included pediatric subjects aged 4 to 11 years and compared fluticasone propionate/salmeterol inhalation powder with fluticasone propionate inhalation powder [see Clinical Studies (14.1)]. The primary safety endpoint for all 4 trials was serious asthma-related events (hospitalizations, intubations, death). A blinded adjudication committee determined whether events were asthma related.

The 3 adult and adolescent trials were designed to rule out a risk margin of 2.0, and the pediatric trial was designed to rule out a risk margin of 2.7. Each individual trial met its pre-specified objective and demonstrated non-inferiority of ICS/LABA to ICS alone. A meta-analysis of the 3 adult and adolescent trials did not show a significant increase in risk of a serious asthma-related event with ICS/LABA fixed-dose combination compared with ICS alone (Table 1). These trials were not designed to rule out all risk for serious asthma-related events with ICS/LABA compared with ICS.

Table 1. Meta-analysis of Serious Asthma-Related Events in Subjects with Asthma Aged 12 Years and Older
 | ICS/LABA; (n = 17,537)a | ICS; (n = 17,552)a | ICS/LABA vs. ICS; Hazard Ratio (95% CI)b
Serious asthma-related eventc | 116 | 105 | 1.10 (0.85, 1.44)
Asthma-related death | 2 | 0
Asthma-related intubation (endotracheal) | 1 | 2
Asthma-related hospitalization (≥24-hour stay) | 115 | 105
ICS = Inhaled Corticosteroid, LABA = Long-acting Beta2-adrenergic Agonist.
a Randomized subjects who had taken at least 1 dose of study drug. Planned treatment used for analysis.
b Estimated using a Cox proportional hazards model for time to first event with baseline hazards stratified by each of the 3 trials.
c Number of subjects with event that occurred within 6 months after the first use of study drug or 7 days after the last date of study drug, whichever date was later. Subjects can have one or more events, but only the first event was counted for analysis. A single, blinded, independent adjudication committee determined whether events were asthma related.

The pediatric safety trial included 6,208 pediatric subjects aged 4 to 11 years who received ICS/LABA (fluticasone propionate/salmeterol inhalation powder) or ICS (fluticasone propionate inhalation powder). In this trial, 27/3,107 (0.9%) subjects randomized to ICS/LABA and 21/3,101 (0.7%) subjects randomized to ICS experienced a serious asthma-related event. There were no asthma-related deaths or intubations. ICS/LABA did not show a significantly increased risk of a serious asthma-related event compared with ICS based on the pre-specified risk margin (2.7), with an estimated hazard ratio of time to first event of 1.29 (95% CI: 0.73, 2.27).

Salmeterol Multicenter Asthma Research Trial (SMART)

A 28-week, placebo-controlled, U.S. trial that compared the safety of salmeterol with placebo, each added to usual asthma therapy, showed an increase in asthma-related deaths in subjects receiving salmeterol (13/13,176 in subjects treated with salmeterol versus 3/13,179 in subjects treated with placebo; relative risk: 4.37 [95% CI: 1.25, 15.34]). Use of background ICS was not required in SMART. The increased risk of asthma-related death is considered a class effect of LABA monotherapy.

5.2 Deterioration of Disease and Acute Episodes

ADVAIR DISKUS should not be initiated in patients during rapidly deteriorating or potentially life-threatening episodes of asthma or COPD. ADVAIR DISKUS has not been studied in subjects with acutely deteriorating asthma or COPD. The initiation of ADVAIR DISKUS in this setting is not appropriate.

Serious acute respiratory events, including fatalities, have been reported when salmeterol, a component of ADVAIR DISKUS, has been initiated in patients with significantly worsening or acutely deteriorating asthma. In most cases, these have occurred in patients with severe asthma (e.g., patients with a history of corticosteroid dependence, low pulmonary function, intubation, mechanical ventilation, frequent hospitalizations, previous life-threatening acute asthma exacerbations) and in some patients with acutely deteriorating asthma (e.g., patients with significantly increasing symptoms; increasing need for inhaled, short-acting beta2-agonists; decreasing response to usual medications; increasing need for systemic corticosteroids; recent emergency room visits; deteriorating lung function). However, these events have occurred in a few patients with less severe asthma as well. It was not possible from these reports to determine whether salmeterol contributed to these events.

Increasing use of inhaled, short-acting beta2-agonists is a marker of deteriorating asthma. In this situation, the patient requires immediate reevaluation with reassessment of the treatment regimen, giving special consideration to the possible need for replacing the current strength of ADVAIR DISKUS with a higher strength, adding additional ICS, or initiating systemic corticosteroids. Patients should not use more than 1 inhalation twice daily of ADVAIR DISKUS.

ADVAIR DISKUS should not be used for the relief of acute symptoms, i.e., as rescue therapy for the treatment of acute episodes of bronchospasm. ADVAIR DISKUS has not been studied in the relief of acute symptoms and extra doses should not be used for that purpose. Acute symptoms should be treated with an inhaled, short-acting beta2-agonist.

When beginning treatment with ADVAIR DISKUS, patients who have been taking oral or inhaled, short-acting beta2-agonists on a regular basis (e.g., 4 times a day) should be instructed to discontinue the regular use of these drugs.

5.3 Excessive Use of ADVAIR DISKUS and Use with Other Long-acting Beta2-agonists

ADVAIR DISKUS should not be used more often than recommended, at higher doses than recommended, or in conjunction with other medicines containing LABA, as an overdose may result. Clinically significant cardiovascular effects and fatalities have been reported in association with excessive use of inhaled sympathomimetic drugs. Patients using ADVAIR DISKUS should not use another medicine containing a LABA (e.g., salmeterol, formoterol fumarate, arformoterol tartrate, indacaterol) for any reason.

5.4 Local Effects of Inhaled Corticosteroids

In clinical trials, the development of localized infections of the mouth and pharynx with Candida albicans has occurred in subjects treated with ADVAIR DISKUS. When such an infection develops, it should be treated with appropriate local or systemic (i.e., oral) antifungal therapy while treatment with ADVAIR DISKUS continues, but at times therapy with ADVAIR DISKUS may need to be interrupted. Advise the patient to rinse his/her mouth with water without swallowing following inhalation to help reduce the risk of oropharyngeal candidiasis.

5.5 Pneumonia

Physicians should remain vigilant for the possible development of pneumonia in patients with COPD as the clinical features of pneumonia and exacerbations frequently overlap.

Lower respiratory tract infections, including pneumonia, have been reported in patients with COPD following the inhaled administration of corticosteroids, including fluticasone propionate and ADVAIR DISKUS. In 2 replicate 1-year trials in 1,579 subjects with COPD, there was a higher incidence of pneumonia reported in subjects receiving ADVAIR DISKUS 250/50 (7%) than in those receiving salmeterol 50 mcg (3%). The incidence of pneumonia in the subjects treated with ADVAIR DISKUS was higher in subjects older than 65 years (9%) compared with the incidence in subjects younger than 65 years (4%). [See Adverse Reactions (6.2), Use in Specific Populations (8.5).]

In a 3-year trial in 6,184 subjects with COPD, there was a higher incidence of pneumonia reported in subjects receiving ADVAIR DISKUS 500/50 compared with placebo (16% with ADVAIR DISKUS 500/50, 14% with fluticasone propionate 500 mcg, 11% with salmeterol 50 mcg, and 9% with placebo). Similar to what was seen in the 1-year trials with ADVAIR DISKUS 250/50, the incidence of pneumonia was higher in subjects older than 65 years (18% with ADVAIR DISKUS 500/50 versus 10% with placebo) compared with subjects younger than 65 years (14% with ADVAIR DISKUS 500/50 versus 8% with placebo). [See Adverse Reactions (6.2), Use in Specific Populations (8.5).]

5.6 Immunosuppression

Persons who are using drugs that suppress the immune system are more susceptible to infections than healthy individuals. Chickenpox and measles, for example, can have a more serious or even fatal course in susceptible children or adults using corticosteroids. In such children or adults who have not had these diseases or been properly immunized, particular care should be taken to avoid exposure. How the dose, route, and duration of corticosteroid administration affect the risk of developing a disseminated infection is not known. The contribution of the underlying disease and/or prior corticosteroid treatment to the risk is also not known. If a patient is exposed to chickenpox, prophylaxis with varicella zoster immune globulin (VZIG) may be indicated. If a patient is exposed to measles, prophylaxis with pooled intramuscular immunoglobulin (IG) may be indicated. (See the respective package inserts for complete VZIG and IG prescribing information.) If chickenpox develops, treatment with antiviral agents may be considered.

ICS should be used with caution, if at all, in patients with active or quiescent tuberculosis infections of the respiratory tract; systemic fungal, bacterial, viral, or parasitic infections; or ocular herpes simplex.

5.7 Transferring Patients from Systemic Corticosteroid Therapy

Particular care is needed for patients who have been transferred from systemically active corticosteroids to ICS because deaths due to adrenal insufficiency have occurred in patients with asthma during and after transfer from systemic corticosteroids to less systemically available ICS. After withdrawal from systemic corticosteroids, a number of months are required for recovery of hypothalamic-pituitary-adrenal (HPA) function.

Patients who have been previously maintained on 20 mg or more of prednisone (or its equivalent) may be most susceptible, particularly when their systemic corticosteroids have been almost completely withdrawn. During this period of HPA suppression, patients may exhibit signs and symptoms of adrenal insufficiency when exposed to trauma, surgery, or infection (particularly gastroenteritis) or other conditions associated with severe electrolyte loss. Although ADVAIR DISKUS may control asthma symptoms during these episodes, in recommended doses it supplies less than normal physiological amounts of glucocorticoid systemically and does NOT provide the mineralocorticoid activity that is necessary for coping with these emergencies.

During periods of stress or a severe asthma attack, patients who have been withdrawn from systemic corticosteroids should be instructed to resume oral corticosteroids (in large doses) immediately and to contact their physicians for further instruction. These patients should also be instructed to carry a warning card indicating that they may need supplementary systemic corticosteroids during periods of stress or a severe asthma attack.

Patients requiring oral corticosteroids should be weaned slowly from systemic corticosteroid use after transferring to ADVAIR DISKUS. Prednisone reduction can be accomplished by reducing the daily prednisone dose by 2.5 mg on a weekly basis during therapy with ADVAIR DISKUS. Lung function (mean forced expiratory volume in 1 second [FEV1] or morning peak expiratory flow [AM PEF]), beta-agonist use, and asthma symptoms should be carefully monitored during withdrawal of oral corticosteroids. In addition, patients should be observed for signs and symptoms of adrenal insufficiency, such as fatigue, lassitude, weakness, nausea and vomiting, and hypotension.

Transfer of patients from systemic corticosteroid therapy to ADVAIR DISKUS may unmask allergic conditions previously suppressed by the systemic corticosteroid therapy (e.g., rhinitis, conjunctivitis, eczema, arthritis, eosinophilic conditions).

During withdrawal from oral corticosteroids, some patients may experience symptoms of systemically active corticosteroid withdrawal (e.g., joint and/or muscular pain, lassitude, depression) despite maintenance or even improvement of respiratory function.

5.8 Hypercorticism and Adrenal Suppression

Fluticasone propionate, a component of ADVAIR DISKUS, will often help control asthma symptoms with less suppression of HPA function than therapeutically equivalent oral doses of prednisone. Since fluticasone propionate is absorbed into the circulation and can be systemically active at higher doses, the beneficial effects of ADVAIR DISKUS in minimizing HPA dysfunction may be expected only when recommended dosages are not exceeded and individual patients are titrated to the lowest effective dose. A relationship between plasma levels of fluticasone propionate and inhibitory effects on stimulated cortisol production has been shown after 4 weeks of treatment with fluticasone propionate inhalation aerosol. Since individual sensitivity to effects on cortisol production exists, physicians should consider this information when prescribing ADVAIR DISKUS.

Because of the possibility of significant systemic absorption of ICS in sensitive patients, patients treated with ADVAIR DISKUS should be observed carefully for any evidence of systemic corticosteroid effects. Particular care should be taken in observing patients postoperatively or during periods of stress for evidence of inadequate adrenal response.

It is possible that systemic corticosteroid effects such as hypercorticism and adrenal suppression (including adrenal crisis) may appear in a small number of patients who are sensitive to these effects. If such effects occur, ADVAIR DISKUS should be reduced slowly, consistent with accepted procedures for reducing systemic corticosteroids, and other treatments for management of asthma symptoms should be considered.

5.9 Drug Interactions with Strong Cytochrome P450 3A4 Inhibitors

The use of strong cytochrome P450 3A4 (CYP3A4) inhibitors (e.g., ritonavir, atazanavir, clarithromycin, indinavir, itraconazole, nefazodone, nelfinavir, saquinavir, ketoconazole, telithromycin) with ADVAIR DISKUS is not recommended because increased systemic corticosteroid and increased cardiovascular adverse effects may occur [see Drug Interactions (7.1), Clinical Pharmacology (12.3)].

5.10 Paradoxical Bronchospasm and Upper Airway Symptoms

As with other inhaled medicines, ADVAIR DISKUS can produce paradoxical bronchospasm, which may be life threatening. If paradoxical bronchospasm occurs following dosing with ADVAIR DISKUS, it should be treated immediately with an inhaled, short-acting bronchodilator; ADVAIR DISKUS should be discontinued immediately; and alternative therapy should be instituted. Upper airway symptoms of laryngeal spasm, irritation, or swelling, such as stridor and choking, have been reported in patients receiving ADVAIR DISKUS.

5.11 Immediate Hypersensitivity Reactions

Immediate hypersensitivity reactions (e.g., urticaria, angioedema, rash, bronchospasm, hypotension), including anaphylaxis, may occur after administration of ADVAIR DISKUS. There have been reports of anaphylactic reactions in patients with severe milk protein allergy after inhalation of powder products containing lactose; therefore, patients with severe milk protein allergy should not use ADVAIR DISKUS [see Contraindications (4)].

5.12 Cardiovascular and Central Nervous System Effects

Excessive beta-adrenergic stimulation has been associated with seizures, angina, hypertension or hypotension, tachycardia with rates up to 200 beats/min, arrhythmias, nervousness, headache, tremor, palpitation, nausea, dizziness, fatigue, malaise, and insomnia [see Overdosage (10.2)]. Therefore, ADVAIR DISKUS, like all products containing sympathomimetic amines, should be used with caution in patients with cardiovascular disorders, especially coronary insufficiency, cardiac arrhythmias, and hypertension.

Salmeterol, a component of ADVAIR DISKUS, can produce a clinically significant cardiovascular effect in some patients as measured by pulse rate, blood pressure, and/or symptoms. Although such effects are uncommon after administration of salmeterol at recommended doses, if they occur, the drug may need to be discontinued. In addition, beta-agonists have been reported to produce electrocardiogram (ECG) changes, such as flattening of the T wave, prolongation of the QTc interval, and ST segment depression. The clinical significance of these findings is unknown. Large doses of inhaled or oral salmeterol (12 to 20 times the recommended dose) have been associated with clinically significant prolongation of the QTc interval, which has the potential for producing ventricular arrhythmias. Fatalities have been reported in association with excessive use of inhaled sympathomimetic drugs.

5.13 Reduction in Bone Mineral Density

Decreases in bone mineral density (BMD) have been observed with long-term administration of products containing ICS. The clinical significance of small changes in BMD with regard to long-term consequences such as fracture is unknown. Patients with major risk factors for decreased bone mineral content, such as prolonged immobilization, family history of osteoporosis, postmenopausal status, tobacco use, advanced age, poor nutrition, or chronic use of drugs that can reduce bone mass (e.g., anticonvulsants, oral corticosteroids), should be monitored and treated with established standards of care. Since patients with COPD often have multiple risk factors for reduced BMD, assessment of BMD is recommended prior to initiating ADVAIR DISKUS and periodically thereafter. If significant reductions in BMD are seen and ADVAIR DISKUS is still considered medically important for that patient’s COPD therapy, use of medicine to treat or prevent osteoporosis should be strongly considered.

2-Year Fluticasone Propionate Trial

A 2-year trial in 160 subjects (females aged 18 to 40 years, males 18 to 50) with asthma receiving chlorofluorocarbon (CFC)-propelled fluticasone propionate inhalation aerosol 88 or 440 mcg twice daily demonstrated no statistically significant changes in BMD at any time point (24, 52, 76, and 104 weeks of double-blind treatment) as assessed by dual-energy x-ray absorptiometry at lumbar regions L1 through L4.

3-Year Bone Mineral Density Trial

Effects of treatment with ADVAIR DISKUS 250/50 or salmeterol 50 mcg on BMD at the L1-L4 lumbar spine and total hip were evaluated in 186 subjects with COPD (aged 43 to 87 years) in a 3-year double-blind trial. Of those enrolled, 108 subjects (72 males and 36 females) were followed for the entire 3 years. BMD evaluations were conducted at baseline and at 6-month intervals. Conclusions cannot be drawn from this trial regarding BMD decline in subjects treated with ADVAIR DISKUS versus salmeterol due to the inconsistency of treatment differences across gender and between lumbar spine and total hip.

In this trial there were 7 non-traumatic fractures reported in 5 subjects treated with ADVAIR DISKUS and 1 non-traumatic fracture in 1 subject treated with salmeterol. None of the non-traumatic fractures occurred in the vertebrae, hip, or long bones.

3-Year Survival Trial

Effects of treatment with ADVAIR DISKUS 500/50, fluticasone propionate 500 mcg, salmeterol 50 mcg, or placebo on BMD was evaluated in a subset of 658 subjects (females and males aged 40 to 80 years) with COPD in the 3-year survival trial. BMD evaluations were conducted at baseline and at 48, 108, and 158 weeks. Conclusions cannot be drawn from this trial because of the large number of dropouts (>50%) before the end of the follow-up and the maldistribution of covariates among the treatment groups that can affect BMD.

Fracture risk was estimated for the entire population of subjects with COPD in the survival trial (N = 6,184). The probability of a fracture over 3 years was 6.3% for ADVAIR DISKUS, 5.4% for fluticasone propionate, 5.1% for salmeterol, and 5.1% for placebo.

5.14 Effect on Growth

Orally inhaled corticosteroids may cause a reduction in growth velocity when administered to pediatric patients. Monitor the growth of pediatric patients receiving ADVAIR DISKUS routinely (e.g., via stadiometry). To minimize the systemic effects of orally inhaled corticosteroids, including ADVAIR DISKUS, titrate each patient’s dosage to the lowest dosage that effectively controls his/her symptoms [see Dosage and Administration (2.1), Use in Specific Populations (8.4)].

5.15 Glaucoma and Cataracts

Glaucoma, increased intraocular pressure, and cataracts have been reported in patients with asthma and COPD following the long-term administration of ICS, including fluticasone propionate, a component of ADVAIR DISKUS. Consider referral to an ophthalmologist in patients who develop ocular symptoms or use ADVAIR DISKUS long term.

Effects of treatment with ADVAIR DISKUS 500/50, fluticasone propionate 500 mcg, salmeterol 50 mcg, or placebo on development of cataracts or glaucoma was evaluated in a subset of 658 subjects with COPD in the 3-year survival trial. Ophthalmic examinations were conducted at baseline and at 48, 108, and 158 weeks. Conclusions about cataracts cannot be drawn from this trial because the high incidence of cataracts at baseline (61% to 71%) resulted in an inadequate number of subjects treated with ADVAIR DISKUS 500/50 who were eligible and available for evaluation of cataracts at the end of the trial (n = 53). The incidence of newly diagnosed glaucoma was 2% with ADVAIR DISKUS 500/50, 5% with fluticasone propionate, 0% with salmeterol, and 2% with placebo.

5.16 Eosinophilic Conditions and Churg-Strauss Syndrome

In rare cases, patients on inhaled fluticasone propionate, a component of ADVAIR DISKUS, may present with systemic eosinophilic conditions. Some of these patients have clinical features of vasculitis consistent with Churg-Strauss syndrome, a condition that is often treated with systemic corticosteroid therapy. These events usually, but not always, have been associated with the reduction and/or withdrawal of oral corticosteroid therapy following the introduction of fluticasone propionate. Cases of serious eosinophilic conditions have also been reported with other ICS in this clinical setting. Physicians should be alert to eosinophilia, vasculitic rash, worsening pulmonary symptoms, cardiac complications, and/or neuropathy presenting in their patients. A causal relationship between fluticasone propionate and these underlying conditions has not been established.

5.17 Coexisting Conditions

ADVAIR DISKUS, like all medicines containing sympathomimetic amines, should be used with caution in patients with convulsive disorders or thyrotoxicosis and in those who are unusually responsive to sympathomimetic amines. Doses of the related beta2-adrenoceptor agonist albuterol, when administered intravenously, have been reported to aggravate preexisting diabetes mellitus and ketoacidosis.

5.18 Hypokalemia and Hyperglycemia

Beta-adrenergic agonist medicines may produce significant hypokalemia in some patients, possibly through intracellular shunting, which has the potential to produce adverse cardiovascular effects [see Clinical Pharmacology (12.2)]. The decrease in serum potassium is usually transient, not requiring supplementation. Clinically significant changes in blood glucose and/or serum potassium were seen infrequently during clinical trials with ADVAIR DISKUS at recommended doses.

6 ADVERSE REACTIONS

6.1 Clinical Trials Experience in Asthma

Adult and Adolescent Subjects Aged 12 Years and Older

The incidence of adverse reactions associated with ADVAIR DISKUS in Table 2 is based upon two 12-week, placebo-controlled, U.S. clinical trials (Trials 1 and 2). A total of 705 adult and adolescent subjects (349 females and 356 males) previously treated with salmeterol or ICS were treated twice daily with ADVAIR DISKUS (100/50- or 250/50-mcg doses), fluticasone propionate inhalation powder (100- or 250-mcg doses), salmeterol inhalation powder 50 mcg, or placebo. The average duration of exposure was 60 to 79 days in the active treatment groups compared with 42 days in the placebo group.

Table 2. Adverse Reactions with ADVAIR DISKUS with ≥3% Incidence and More Common than Placebo in Adult and Adolescent Subjects with Asthma
Adverse Event | ADVAIR DISKUS 100/50; (n = 92); % | ADVAIR DISKUS 250/50; (n = 84); % | Fluticasone Propionate 100 mcg; (n = 90); % | Fluticasone Propionate 250 mcg; (n = 84); % | Salmeterol 50 mcg; (n = 180); % | Placebo (n = 175); %
Ear, nose, and throat
Upper respiratory tract infection | 27 | 21 | 29 | 25 | 19 | 14
Pharyngitis | 13 | 10 | 7 | 12 | 8 | 6
Upper respiratory inflammation | 7 | 6 | 7 | 8 | 8 | 5
Sinusitis | 4 | 5 | 6 | 1 | 3 | 4
Hoarseness/dysphonia | 5 | 2 | 2 | 4 | <1 | <1
Oral candidiasis | 1 | 4 | 2 | 2 | 0 | 0
Lower respiratory
Viral respiratory infections | 4 | 4 | 4 | 10 | 6 | 3
Bronchitis | 2 | 8 | 1 | 2 | 2 | 2
Cough | 3 | 6 | 0 | 0 | 3 | 2
Neurology
Headaches | 12 | 13 | 14 | 8 | 10 | 7
Gastrointestinal
Nausea and vomiting | 4 | 6 | 3 | 4 | 1 | 1
Gastrointestinal discomfort and pain | 4 | 1 | 0 | 2 | 1 | 1
Diarrhea | 4 | 2 | 2 | 2 | 1 | 1
Viral gastrointestinal infections | 3 | 0 | 3 | 1 | 2 | 2
Non-site specific
Candidiasis unspecified site | 3 | 0 | 1 | 4 | 0 | 1
Musculoskeletal
Musculoskeletal pain | 4 | 2 | 1 | 5 | 3 | 3

The types of adverse reactions and events reported in Trial 3, a 28-week, non-U.S. clinical trial in 503 subjects previously treated with ICS who were treated twice daily with ADVAIR DISKUS 500/50, fluticasone propionate inhalation powder 500 mcg and salmeterol inhalation powder 50 mcg used concurrently, or fluticasone propionate inhalation powder 500 mcg, were similar to those reported in Table 2.

Additional Adverse Reactions

Other adverse reactions not previously listed, whether considered drug-related or not by the investigators, that were reported more frequently by subjects with asthma treated with ADVAIR DISKUS compared with subjects treated with placebo include the following: lymphatic signs and symptoms; muscle injuries; fractures; wounds and lacerations; contusions and hematomas; ear signs and symptoms; nasal signs and symptoms; nasal sinus disorders; keratitis and conjunctivitis; dental discomfort and pain; gastrointestinal signs and symptoms; oral ulcerations; oral discomfort and pain; lower respiratory signs and symptoms; pneumonia; muscle stiffness, tightness, and rigidity; bone and cartilage disorders; sleep disorders; compressed nerve syndromes; viral infections; pain; chest symptoms; fluid retention; bacterial infections; unusual taste; viral skin infections; skin flakiness and acquired ichthyosis; disorders of sweat and sebum.

Pediatric Subjects Aged 4 to 11 Years

The safety data for pediatric subjects aged 4 to 11 years is based upon 1 U.S. trial of 12 weeks’ treatment duration. A total of 203 subjects (74 females and 129 males) who were receiving ICS at trial entry were randomized to either ADVAIR DISKUS 100/50 or fluticasone propionate inhalation powder 100 mcg twice daily. Common adverse reactions (≥3% and greater than placebo) seen in the pediatric subjects but not reported in the adult and adolescent clinical trials include: throat irritation and ear, nose, and throat infections.

Laboratory Test Abnormalities

Elevation of hepatic enzymes was reported in ≥1% of subjects in clinical trials. The elevations were transient and did not lead to discontinuation from the trials. In addition, there were no clinically relevant changes noted in glucose or potassium.

6.2 Clinical Trials Experience in Chronic Obstructive Pulmonary Disease

Short-term (6 Months to 1 Year) Trials

The short-term safety data are based on exposure to ADVAIR DISKUS 250/50 twice daily in one 6-month and two 1-year clinical trials. In the 6-month trial, a total of 723 adult subjects (266 females and 457 males) were treated twice daily with ADVAIR DISKUS 250/50, fluticasone propionate inhalation powder 250 mcg, salmeterol inhalation powder, or placebo. The mean age of the subjects was 64, and the majority (93%) was Caucasian. In this trial, 70% of the subjects treated with ADVAIR DISKUS reported an adverse reaction compared with 64% on placebo. The average duration of exposure to ADVAIR DISKUS 250/50 was 141.3 days compared with 131.6 days for placebo. The incidence of adverse reactions in the 6-month trial is shown in Table 3.

Table 3. Overall Adverse Reactions with ADVAIR DISKUS 250/50 with ≥3% Incidence in Subjects with Chronic Obstructive Pulmonary Disease Associated with Chronic Bronchitis
Adverse Event | ADVAIR DISKUS 250/50; (n = 178); % | Fluticasone Propionate 250 mcg; (n = 183); % | Salmeterol 50 mcg; (n = 177); % | Placebo (n = 185); %
Ear, nose, and throat
Candidiasis mouth/throat | 10 | 6 | 3 | 1
Throat irritation | 8 | 5 | 4 | 7
Hoarseness/dysphonia | 5 | 3 | <1 | 0
Sinusitis | 3 | 8 | 5 | 3
Lower respiratory
Viral respiratory infections | 6 | 4 | 3 | 3
Neurology
Headaches | 16 | 11 | 10 | 12
Dizziness | 4 | <1 | 3 | 2
Non-site specific
Fever | 4 | 3 | 0 | 3
Malaise and fatigue | 3 | 2 | 2 | 3
Musculoskeletal
Musculoskeletal pain | 9 | 8 | 12 | 9
Muscle cramps and spasms | 3 | 3 | 1 | 1

In the two 1-year trials, ADVAIR DISKUS 250/50 was compared with salmeterol in 1,579 subjects (863 males and 716 females). The mean age of the subjects was 65 years, and the majority (94%) was Caucasian. To be enrolled, all of the subjects had to have had a COPD exacerbation in the previous 12 months. In this trial, 88% of the subjects treated with ADVAIR DISKUS and 86% of the subjects treated with salmeterol reported an adverse event. The most common events that occurred with a frequency of >5% and more frequently in the subjects treated with ADVAIR DISKUS were nasopharyngitis, upper respiratory tract infection, nasal congestion, back pain, sinusitis, dizziness, nausea, pneumonia, candidiasis, and dysphonia. Overall, 55 (7%) of the subjects treated with ADVAIR DISKUS and 25 (3%) of the subjects treated with salmeterol developed pneumonia.

The incidence of pneumonia was higher in subjects older than 65 years, 9% in the subjects treated with ADVAIR DISKUS compared with 4% in the subjects treated with ADVAIR DISKUS younger than 65 years. In the subjects treated with salmeterol, the incidence of pneumonia was the same (3%) in both age groups. [See Warnings and Precautions (5.5), Use in Specific Populations (8.5).]

Long-term (3 Years) Trial

The safety of ADVAIR DISKUS 500/50 was evaluated in a randomized, double-blind, placebo-controlled, multicenter, international, 3-year trial in 6,184 adult subjects with COPD (4,684 males and 1,500 females). The mean age of the subjects was 65 years, and the majority (82%) was Caucasian. The distribution of adverse events was similar to that seen in the 1-year trials with ADVAIR DISKUS 250/50. In addition, pneumonia was reported in a significantly increased number of subjects treated with ADVAIR DISKUS 500/50 and fluticasone propionate 500 mcg (16% and 14%, respectively) compared with subjects treated with salmeterol 50 mcg or placebo (11% and 9%, respectively). When adjusted for time on treatment, the rates of pneumonia were 84 and 88 events per 1,000 treatment-years in the groups treated with fluticasone propionate 500 mcg and with ADVAIR DISKUS 500/50, respectively, compared with 52 events per 1,000 treatment-years in the salmeterol and placebo groups. Similar to what was seen in the 1-year trials with ADVAIR DISKUS 250/50, the incidence of pneumonia was higher in subjects older than 65 years (18% with ADVAIR DISKUS 500/50 versus 10% with placebo) compared with subjects younger than 65 years (14% with ADVAIR DISKUS 500/50 versus 8% with placebo). [See Warnings and Precautions (5.5), Use in Specific Populations (8.5).]

Additional Adverse Reactions

Other adverse reactions not previously listed, whether considered drug-related or not by the investigators, that were reported more frequently by subjects with COPD treated with ADVAIR DISKUS compared with subjects treated with placebo include the following: syncope; ear, nose, and throat infections; ear signs and symptoms; laryngitis; nasal congestion/blockage; nasal sinus disorders; pharyngitis/throat infection; hypothyroidism; dry eyes; eye infections; gastrointestinal signs and symptoms; oral lesions; abnormal liver function tests; bacterial infections; edema and swelling; viral infections.

Laboratory Abnormalities

There were no clinically relevant changes in these trials. Specifically, no increased reporting of neutrophilia or changes in glucose or potassium was noted.

6.3 Postmarketing Experience

In addition to adverse reactions reported from clinical trials, the following adverse reactions have been identified during postapproval use of any formulation of ADVAIR, fluticasone propionate, and/or salmeterol regardless of indication. Because these reactions are reported voluntarily from a population of uncertain size, it is not always possible to reliably estimate their frequency or establish a causal relationship to drug exposure. These events have been chosen for inclusion due to either their seriousness, frequency of reporting, or causal connection to ADVAIR DISKUS, fluticasone propionate, and/or salmeterol or a combination of these factors.

Cardiac Disorders

Arrhythmias (including atrial fibrillation, extrasystoles, supraventricular tachycardia), ventricular tachycardia.

Endocrine Disorders

Cushing’s syndrome, Cushingoid features, growth velocity reduction in children/adolescents, hypercorticism.

Eye Disorders

Glaucoma.

Gastrointestinal Disorders

Abdominal pain, dyspepsia, xerostomia.

Immune System Disorders

Immediate and delayed hypersensitivity reaction (including very rare anaphylactic reaction). Very rare anaphylactic reaction in patients with severe milk protein allergy.

Infections and Infestations

Esophageal candidiasis.

Metabolic and Nutrition Disorders

Hyperglycemia, weight gain.

Musculoskeletal, Connective Tissue, and Bone Disorders

Arthralgia, cramps, myositis, osteoporosis.

Nervous System Disorders

Paresthesia, restlessness.

Psychiatric Disorders

Agitation, aggression, depression. Behavioral changes, including hyperactivity and irritability, have been reported very rarely and primarily in children.

Reproductive System and Breast Disorders

Dysmenorrhea.

Respiratory, Thoracic, and Mediastinal Disorders

Chest congestion; chest tightness; dyspnea; facial and oropharyngeal edema, immediate bronchospasm; paradoxical bronchospasm; tracheitis; wheezing; reports of upper respiratory symptoms of laryngeal spasm, irritation, or swelling such as stridor or choking.

Skin and Subcutaneous Tissue Disorders

Ecchymoses, photodermatitis.

Vascular Disorders

Pallor.

7 DRUG INTERACTIONS

ADVAIR DISKUS has been used concomitantly with other drugs, including short-acting beta2-agonists, methylxanthines, and intranasal corticosteroids, commonly used in patients with asthma or COPD without adverse drug reactions [see Clinical Pharmacology (12.2)]. No formal drug interaction trials have been performed with ADVAIR DISKUS.

7.1 Inhibitors of Cytochrome P450 3A4

Fluticasone propionate and salmeterol, the individual components of ADVAIR DISKUS, are substrates of CYP3A4. The use of strong CYP3A4 inhibitors (e.g., ritonavir, atazanavir, clarithromycin, indinavir, itraconazole, nefazodone, nelfinavir, saquinavir, ketoconazole, telithromycin) with ADVAIR DISKUS is not recommended because increased systemic corticosteroid and increased cardiovascular adverse effects may occur.

Ritonavir

Fluticasone Propionate: A drug interaction trial with fluticasone propionate aqueous nasal spray in healthy subjects has shown that ritonavir (a strong CYP3A4 inhibitor) can significantly increase plasma fluticasone propionate exposure, resulting in significantly reduced serum cortisol concentrations [see Clinical Pharmacology (12.3)]. During postmarketing use, there have been reports of clinically significant drug interactions in patients receiving fluticasone propionate and ritonavir, resulting in systemic corticosteroid effects including Cushing’s syndrome and adrenal suppression.

Ketoconazole

Fluticasone Propionate: Coadministration of orally inhaled fluticasone propionate (1,000 mcg) and ketoconazole (200 mg once daily) resulted in a 1.9-fold increase in plasma fluticasone propionate exposure and a 45% decrease in plasma cortisol area under the curve (AUC), but had no effect on urinary excretion of cortisol.

Salmeterol: In a drug interaction trial in 20 healthy subjects, coadministration of inhaled salmeterol (50 mcg twice daily) and oral ketoconazole (400 mg once daily) for 7 days resulted in greater systemic exposure to salmeterol (AUC increased 16-fold and Cmax increased 1.4-fold). Three (3) subjects were withdrawn due to beta2-agonist side effects (2 with prolonged QTc and 1 with palpitations and sinus tachycardia). Although there was no statistical effect on the mean QTc, coadministration of salmeterol and ketoconazole was associated with more frequent increases in QTc duration compared with salmeterol and placebo administration.

7.2 Monoamine Oxidase Inhibitors and Tricyclic Antidepressants

ADVAIR DISKUS should be administered with extreme caution to patients being treated with monoamine oxidase inhibitors or tricyclic antidepressants, or within 2 weeks of discontinuation of such agents, because the action of salmeterol, a component of ADVAIR DISKUS, on the vascular system may be potentiated by these agents.

7.3 Beta-adrenergic Receptor Blocking Agents

Beta-blockers not only block the pulmonary effect of beta-agonists, such as salmeterol, a component of ADVAIR DISKUS, but may also produce severe bronchospasm in patients with asthma or COPD. Therefore, patients with asthma or COPD should not normally be treated with beta-blockers. However, under certain circumstances, there may be no acceptable alternatives to the use of beta-adrenergic blocking agents for these patients; cardioselective beta-blockers could be considered, although they should be administered with caution.

7.4 Non–Potassium-Sparing Diuretics

The ECG changes and/or hypokalemia that may result from the administration of non–potassium-sparing diuretics (such as loop or thiazide diuretics) can be acutely worsened by beta-agonists, such as salmeterol, a component of ADVAIR DISKUS, especially when the recommended dose of the beta-agonist is exceeded. Although the clinical significance of these effects is not known, caution is advised in the coadministration of ADVAIR DISKUS with non–potassium-sparing diuretics.

8 USE IN SPECIFIC POPULATIONS

8.1 Pregnancy

Risk Summary

There are insufficient data on the use of ADVAIR DISKUS or individual monoproducts, fluticasone propionate and salmeterol xinafoate, in pregnant women. There are clinical considerations with the use of ADVAIR DISKUS in pregnant women. (See Clinical Considerations.) In animals, teratogenicity characteristic of corticosteroids, decreased fetal body weight and/or skeletal variations, in rats, mice, and rabbits were observed with subcutaneously administered maternal toxic doses of fluticasone propionate less than the maximum recommended human daily inhaled dose (MRHDID) on a mcg/m^2 basis. (See Data.) However, fluticasone propionate administered via inhalation to rats decreased fetal body weight, but did not induce teratogenicity at a maternal toxic dose less than the MRHDID on a mcg/m^2 basis. (See Data.) Experience with oral corticosteroids suggests that rodents are more prone to teratogenic effects from corticosteroids than humans. Oral administration of salmeterol to pregnant rabbits caused teratogenicity characteristic of beta-adrenoceptor stimulation at maternal doses approximately 50 times the MRHDID on an AUC basis. These adverse effects generally occurred at large multiples of the MRHDID when salmeterol was administered by the oral route to achieve high systemic exposures. No such effects occurred at an oral salmeterol dose approximately 20 times the MRHDID. (See Data.)

The estimated risk of major birth defects and miscarriage for the indicated population is unknown. In the U.S. general population, the estimated risk of major birth defects and miscarriage in clinically recognized pregnancies is 2% to 4% and 15% to 20%, respectively.

Clinical Considerations

Disease-Associated Maternal and/or Embryofetal Risk: In women with poorly or moderately controlled asthma, there is an increased risk of several perinatal outcomes such as pre-eclampsia in the mother and prematurity, low birth weight, and small for gestational age in the neonate. Pregnant women should be closely monitored and medication adjusted as necessary to maintain optimal control of asthma.

Labor and Delivery: There are no human studies evaluating the effects of ADVAIR DISKUS during labor and delivery. Because of the potential for beta-agonist interference with uterine contractility, use of ADVAIR DISKUS during labor should be restricted to those patients in whom the benefits clearly outweigh the risks.

Data

Human Data: Fluticasone Propionate: Following inhaled administration, fluticasone propionate was detected in the neonatal cord blood after delivery.

Animal Data: Fluticasone Propionate and Salmeterol: In an embryofetal development study with pregnant rats that received the combination of subcutaneous administration of fluticasone propionate and oral administration of salmeterol at doses of 0/1,000; 30/0; 10/100; 30/1,000; and 100/10,000 mcg/kg/day (as fluticasone propionate/salmeterol) during the period of organogenesis, findings were generally consistent with the individual monoproducts and there was no exacerbation of expected fetal effects. Omphalocele, increased embryofetal deaths, decreased body weight, and skeletal variations were observed in rat fetuses in the presence of maternal toxicity when combining fluticasone propionate at a dose approximately equivalent to the MRHDID (on a mcg/m^2 basis at a maternal subcutaneous dose of 100 mcg/kg/day) and salmeterol at a dose approximately 970 times the MRHDID (on a mcg/m^2 basis at a maternal oral dose of 10,000 mcg/kg/day). The rat no observed adverse effect level (NOAEL) was observed when combining fluticasone propionate at a dose approximately 0.3 times the MRHDID (on a mcg/m^2 basis at a maternal subcutaneous dose of 30 mcg/kg/day) and salmeterol at a dose approximately 100 times the MRHDID (on a mcg/m^2 basis at a maternal oral dose of 1,000 mcg/kg/day).

In an embryofetal development study with pregnant mice that received the combination of subcutaneous administration of fluticasone propionate and oral administration of salmeterol at doses of 0/1,400; 40/0; 10/200; 40/1,400; or 150/10,000 mcg/kg/day (as fluticasone propionate/salmeterol) during the period of organogenesis, findings were generally consistent with the individual monoproducts and there was no exacerbation of expected fetal effects. Cleft palate, fetal death, increased implantation loss, and delayed ossification were observed in mouse fetuses when combining fluticasone propionate at a dose approximately 0.7 times the MRHDID (on a mcg/m^2 basis at a maternal subcutaneous dose of 150 mcg/kg/day) and salmeterol at a dose approximately 490 times the MRHDID (on a mcg/m^2 basis at a maternal oral dose of 10,000 mcg/kg/day). No developmental toxicity was observed at combination doses of fluticasone propionate up to approximately 0.2 times the MRHDID (on a mcg/m^2 basis at a maternal subcutaneous dose of 40 mcg/kg) and doses of salmeterol up to approximately 70 times the MRHDID (on a mcg/m^2 basis at a maternal oral dose of 1,400 mcg/kg).

Fluticasone Propionate: In embryofetal development studies with pregnant rats and mice dosed by the subcutaneous route throughout the period of organogenesis, fluticasone propionate was teratogenic in both species. Omphalocele, decreased body weight, and skeletal variations were observed in rat fetuses, in the presence of maternal toxicity, at a dose approximately equivalent to the MRHDID (on a mcg/m^2 basis with a maternal subcutaneous dose of 100 mcg/kg/day). The rat NOAEL was observed at approximately 0.3 times the MRHDID (on a mcg/m^2 basis with a maternal subcutaneous dose of 30 mcg/kg/day). Cleft palate and fetal skeletal variations were observed in mouse fetuses at a dose approximately 0.2 times the MRHDID (on a mcg/m^2 basis with a maternal subcutaneous dose of 45 mcg/kg/day). The mouse NOAEL was observed with a dose approximately 0.07 times the MRHDID (on a mcg/m^2 basis with a maternal subcutaneous dose of 15 mcg/kg/day).

In an embryofetal development study with pregnant rats dosed by the inhalation route throughout the period of organogenesis, fluticasone propionate produced decreased fetal body weights and skeletal variations, in the presence of maternal toxicity, at a dose approximately 0.25 times the MRHDID (on a mcg/m^2 basis with a maternal inhalation dose of 25.7 mcg/kg/day); however, there was no evidence of teratogenicity. The NOAEL was observed with a dose approximately 0.05 times the MRHDID (on a mcg/m^2 basis with a maternal inhalation dose of 5.5 mcg/kg/day).

In an embryofetal development study in pregnant rabbits that were dosed by the subcutaneous route throughout organogenesis, fluticasone propionate produced reductions of fetal body weights, in the presence of maternal toxicity, at doses approximately 0.012 times the MRHDID and higher (on a mcg/m^2 basis with a maternal subcutaneous dose of 0.57 mcg/kg/day). Teratogenicity was evident based upon a finding of cleft palate for 1 fetus at a dose approximately 0.08 times the MRHDID (on a mcg/m^2 basis with a maternal subcutaneous dose of 4 mcg/kg/day). The NOAEL was observed in rabbit fetuses with a dose approximately 0.002 times the MRHDID (on a mcg/m^2 basis with a maternal subcutaneous dose of 0.08 mcg/kg/day).

Fluticasone propionate crossed the placenta following subcutaneous administration to mice and rats and oral administration to rabbits.

In a pre- and post-natal development study in pregnant rats dosed by the subcutaneous route from late gestation through delivery and lactation (Gestation Day 17 to Postpartum Day 22), fluticasone propionate was not associated with decreases in pup body weight, and had no effects on developmental landmarks, learning, memory, reflexes, or fertility at doses up to 0.5 times the MRHDID (on a mcg/m^2 basis with maternal subcutaneous doses up to 50 mcg/kg/day).

Salmeterol: In 3 embryofetal development studies, pregnant rabbits received oral administration of salmeterol at doses ranging from 100 to 10,000 mcg/kg/day during the period of organogenesis. In pregnant Dutch rabbits administered salmeterol doses approximately 50 times the MRHDID (on an AUC basis at maternal oral doses of 1,000 mcg/kg/day and higher), fetal toxic effects were observed characteristically resulting from beta-adrenoceptor stimulation. These included precocious eyelid openings, cleft palate, sternebral fusion, limb and paw flexures, and delayed ossification of the frontal cranial bones. No such effects occurred at a salmeterol dose approximately 20 times the MRHDID (on an AUC basis at a maternal oral dose of 600 mcg/kg/day). New Zealand White rabbits were less sensitive since only delayed ossification of the frontal cranial bones was seen at a salmeterol dose approximately 2,000 times the MRHDID (on a mcg/m^2 basis at a maternal oral dose of 10,000 mcg/kg/day).

In 2 embryofetal development studies, pregnant rats received salmeterol by oral administration at doses ranging from 100 to 10,000 mcg/kg/day during the period of organogenesis. Salmeterol produced no maternal toxicity or embryofetal effects at doses up to 973 times the MRHDID (on a mcg/m^2 basis at maternal oral doses up to 10,000 mcg/kg/day).

In a peri- and post-natal development study in pregnant rats dosed by the oral route from late gestation through delivery and lactation, salmeterol at a dose 973 times the MRHDID (on a mcg/m^2 basis with a maternal oral dose of 10,000 mcg/kg/day) was fetotoxic and decreased the fertility of survivors.

Salmeterol xinafoate crossed the placenta following oral administration to mice and rats.

8.2 Lactation

Risk Summary

There are no available data on the presence of fluticasone propionate or salmeterol in human milk, the effects on the breastfed child, or the effects on milk production. Other corticosteroids have been detected in human milk. However, fluticasone propionate and salmeterol concentrations in plasma after inhaled therapeutic doses are low and therefore concentrations in human breast milk are likely to be correspondingly low [see Clinical Pharmacology (12.3)]. The developmental and health benefits of breastfeeding should be considered along with the mother’s clinical need for ADVAIR DISKUS and any potential adverse effects on the breastfed child from ADVAIR DISKUS or from the underlying maternal condition.

Data

Animal Data: Subcutaneous administration of tritiated fluticasone propionate at a dose of 10 mcg/kg/day to lactating rats resulted in measurable levels in milk. Oral administration of salmeterol at a dose of 10,000 mcg/kg/day to lactating rats resulted in measurable levels in milk.

8.4 Pediatric Use

Use of ADVAIR DISKUS 100/50 in patients aged 4 to 11 years is supported by extrapolation of efficacy data from older subjects and by safety and efficacy data from a trial of ADVAIR DISKUS 100/50 in children with asthma aged 4 to 11 years [see Adverse Reactions (6.1), Clinical Pharmacology (12.3), Clinical Studies (14.1)]. The safety and effectiveness of ADVAIR DISKUS in children with asthma younger than 4 years have not been established.

ICS, including fluticasone propionate, a component of ADVAIR DISKUS, may cause a reduction in growth velocity in children and adolescents [see Warnings and Precautions (5.14)]. The growth of pediatric patients receiving orally inhaled corticosteroids, including ADVAIR DISKUS, should be monitored.

A 52-week placebo-controlled trial to assess the potential growth effects of fluticasone propionate inhalation powder (FLOVENT ROTADISK) at 50 and 100 mcg twice daily was conducted in the U.S. in 325 prepubescent children (244 males and 81 females) aged 4 to 11 years. The mean growth velocities at 52 weeks observed in the intent-to-treat population were 6.32 cm/year in the placebo group (n = 76), 6.07 cm/year in the 50-mcg group (n = 98), and 5.66 cm/year in the 100-mcg group (n = 89). An imbalance in the proportion of children entering puberty between groups and a higher dropout rate in the placebo group due to poorly controlled asthma may be confounding factors in interpreting these data. A separate subset analysis of children who remained prepubertal during the trial revealed growth rates at 52 weeks of 6.10 cm/year in the placebo group (n = 57), 5.91 cm/year in the 50-mcg group (n = 74), and 5.67 cm/year in the 100-mcg group (n = 79). In children aged 8.5 years, the mean age of children in this trial, the range for expected growth velocity is: boys – 3rd percentile = 3.8 cm/year, 50th percentile = 5.4 cm/year, and 97th percentile = 7.0 cm/year; girls – 3rd percentile = 4.2 cm/year, 50th percentile = 5.7 cm/year, and 97th percentile = 7.3 cm/year. The clinical relevance of these growth data is not certain.

If a child or adolescent on any corticosteroid appears to have growth suppression, the possibility that he/she is particularly sensitive to this effect of corticosteroids should be considered. The potential growth effects of prolonged treatment should be weighed against the clinical benefits obtained. To minimize the systemic effects of orally inhaled corticosteroids, including ADVAIR DISKUS, each patient should be titrated to the lowest strength that effectively controls his/her asthma [see Dosage and Administration (2.1)].

8.5 Geriatric Use

Clinical trials of ADVAIR DISKUS for asthma did not include sufficient numbers of subjects aged 65 years and older to determine whether older subjects with asthma respond differently than younger subjects.

Of the total number of subjects in clinical trials receiving ADVAIR DISKUS for COPD, 1,621 were aged 65 years and older and 379 were aged 75 years and older. Subjects with COPD aged 65 years and older had a higher incidence of serious adverse events compared with subjects younger than 65 years. Although the distribution of adverse events was similar in the 2 age groups, subjects older than 65 years experienced more severe events. In two 1-year trials, the excess risk of pneumonia that was seen in subjects treated with ADVAIR DISKUS compared with those treated with salmeterol was greater in subjects older than 65 years than in subjects younger than 65 years [see Adverse Reactions (6.2)]. As with other products containing beta2-agonists, special caution should be observed when using ADVAIR DISKUS in geriatric patients who have concomitant cardiovascular disease that could be adversely affected by beta2-agonists. Based on available data for ADVAIR DISKUS or its active components, no adjustment of dosage of ADVAIR DISKUS in geriatric patients is warranted.

No relationship between fluticasone propionate systemic exposure and age was observed in 57 subjects with COPD (aged 40 to 82 years) given 250 or 500 mcg twice daily.

8.6 Hepatic Impairment

Formal pharmacokinetic studies using ADVAIR DISKUS have not been conducted in patients with hepatic impairment. However, since both fluticasone propionate and salmeterol are predominantly cleared by hepatic metabolism, impairment of liver function may lead to accumulation of fluticasone propionate and salmeterol in plasma. Therefore, patients with hepatic disease should be closely monitored.

8.7 Renal Impairment

Formal pharmacokinetic studies using ADVAIR DISKUS have not been conducted in patients with renal impairment.

10 OVERDOSAGE

No human overdosage data has been reported for ADVAIR DISKUS.

ADVAIR DISKUS contains both fluticasone propionate and salmeterol; therefore, the risks associated with overdosage for the individual components described below apply to ADVAIR DISKUS. Treatment of overdosage consists of discontinuation of ADVAIR DISKUS together with institution of appropriate symptomatic and/or supportive therapy. The judicious use of a cardioselective beta-receptor blocker may be considered, bearing in mind that such medication can produce bronchospasm. Cardiac monitoring is recommended in cases of overdosage.

10.1 Fluticasone Propionate

Chronic overdosage of fluticasone propionate may result in signs/symptoms of hypercorticism [see Warnings and Precautions (5.8)]. Inhalation by healthy volunteers of a single dose of 4,000 mcg of fluticasone propionate inhalation powder or single doses of 1,760 or 3,520 mcg of fluticasone propionate CFC inhalation aerosol was well tolerated. Fluticasone propionate given by inhalation aerosol at dosages of 1,320 mcg twice daily for 7 to 15 days to healthy human volunteers was also well tolerated. Repeat oral doses up to 80 mg daily for 10 days in healthy volunteers and repeat oral doses up to 20 mg daily for 42 days in subjects were well tolerated. Adverse reactions were of mild or moderate severity, and incidences were similar in active and placebo treatment groups.

10.2 Salmeterol

The expected signs and symptoms with overdosage of salmeterol are those of excessive beta‑adrenergic stimulation and/or occurrence or exaggeration of any of the signs and symptoms of beta-adrenergic stimulation (e.g., seizures, angina, hypertension or hypotension, tachycardia with rates up to 200 beats/min, arrhythmias, nervousness, headache, tremor, muscle cramps, dry mouth, palpitation, nausea, dizziness, fatigue, malaise, insomnia, hyperglycemia, hypokalemia, metabolic acidosis). Overdosage with salmeterol can lead to clinically significant prolongation of the QTc interval, which can produce ventricular arrhythmias.

As with all inhaled sympathomimetic medicines, cardiac arrest and even death may be associated with an overdose of salmeterol.

11 DESCRIPTION

ADVAIR DISKUS 100/50, ADVAIR DISKUS 250/50, and ADVAIR DISKUS 500/50 are combinations of fluticasone propionate and salmeterol xinafoate.

One active component of ADVAIR DISKUS is fluticasone propionate, a corticosteroid having the chemical name S-(fluoromethyl) 6α,9-difluoro-11β,17-dihydroxy-16α-methyl-3-oxoandrosta-1,4-diene-17β-carbothioate, 17-propionate and the following chemical structure:

Fluticasone propionate is a white powder with a molecular weight of 500.6, and the empirical formula is C25H31F3O5S. It is practically insoluble in water, freely soluble in dimethyl sulfoxide and dimethylformamide, and slightly soluble in methanol and 95% ethanol.

The other active component of ADVAIR DISKUS is salmeterol xinafoate, a beta2-adrenergic bronchodilator. Salmeterol xinafoate is the racemic form of the 1-hydroxy-2-naphthoic acid salt of salmeterol. It has the chemical name 4-hydroxy-α^1-[[[6-(4-phenylbutoxy)hexyl]amino]methyl]-1,3-benzenedimethanol, 1-hydroxy-2-naphthalenecarboxylate and the following chemical structure:

Salmeterol xinafoate is a white powder with a molecular weight of 603.8, and the empirical formula is C25H37NO4•C11H8O3. It is freely soluble in methanol; slightly soluble in ethanol, chloroform, and isopropanol; and sparingly soluble in water.

ADVAIR DISKUS is a purple plastic inhaler containing a foil blister strip. Each blister on the strip contains a white powder mix of micronized fluticasone propionate (100, 250, or 500 mcg) and micronized salmeterol xinafoate salt (72.5 mcg, equivalent to 50 mcg of salmeterol base) in 12.5 mg of formulation containing lactose monohydrate (which contains milk proteins). After the inhaler is activated, the powder is dispersed into the airstream created by the patient inhaling through the mouthpiece.

Under standardized in vitro test conditions, ADVAIR DISKUS delivers 93, 233, and 465 mcg of fluticasone propionate and 45 mcg of salmeterol base per blister from ADVAIR DISKUS 100/50, ADVAIR DISKUS 250/50, and ADVAIR DISKUS 500/50, respectively, when tested at a flow rate of 60 L/min for 2 seconds.

In adult subjects with obstructive lung disease and severely compromised lung function (mean FEV1 20% to 30% of predicted), mean peak inspiratory flow (PIF) through the DISKUS inhaler was 82.4 L/min (range: 46.1 to 115.3 L/min).

Inhalation profiles for adolescent (N = 13, aged 12 to 17 years) and adult (N = 17, aged 18 to 50 years) subjects with asthma inhaling maximally through the DISKUS inhaler show mean PIF of 122.2 L/min (range: 81.6 to 152.1 L/min). Inhalation profiles for pediatric subjects with asthma inhaling maximally through the DISKUS inhaler show a mean PIF of 75.5 L/min (range: 49.0 to 104.8 L/min) for the 4-year-old subject set (N = 20) and 107.3 L/min (range: 82.8 to 125.6 L/min) for the 8-year-old subject set (N = 20).

The actual amount of drug delivered to the lung will depend on patient factors, such as inspiratory flow profile.

12 CLINICAL PHARMACOLOGY

12.1 Mechanism of Action

ADVAIR DISKUS

ADVAIR DISKUS contains both fluticasone propionate and salmeterol. The mechanisms of action described below for the individual components apply to ADVAIR DISKUS. These drugs represent 2 different classes of medications (a synthetic corticosteroid and a LABA) that have different effects on clinical, physiologic, and inflammatory indices.

Fluticasone Propionate

Fluticasone propionate is a synthetic trifluorinated corticosteroid with anti-inflammatory activity. Fluticasone propionate has been shown in vitro to exhibit a binding affinity for the human glucocorticoid receptor that is 18 times that of dexamethasone, almost twice that of beclomethasone-17-monopropionate (BMP), the active metabolite of beclomethasone dipropionate, and over 3 times that of budesonide. Data from the McKenzie vasoconstrictor assay in man are consistent with these results. The clinical significance of these findings is unknown.

Inflammation is an important component in the pathogenesis of asthma. Corticosteroids have been shown to have a wide range of actions on multiple cell types (e.g., mast cells, eosinophils, neutrophils, macrophages, lymphocytes) and mediators (e.g., histamine, eicosanoids, leukotrienes, cytokines) involved in inflammation. These anti-inflammatory actions of corticosteroids contribute to their efficacy in asthma.

Inflammation is also a component in the pathogenesis of COPD. In contrast to asthma, however, the predominant inflammatory cells in COPD include neutrophils, CD8+ T-lymphocytes, and macrophages. The effects of corticosteroids in the treatment of COPD are not well defined and ICS and fluticasone propionate when used apart from ADVAIR DISKUS are not indicated for the treatment of COPD.

Salmeterol Xinafoate

Salmeterol is a selective LABA. In vitro studies show salmeterol to be at least 50 times more selective for beta2-adrenoceptors than albuterol. Although beta2-adrenoceptors are the predominant adrenergic receptors in bronchial smooth muscle and beta1-adrenoceptors are the predominant receptors in the heart, there are also beta2-adrenoceptors in the human heart comprising 10% to 50% of the total beta-adrenoceptors. The precise function of these receptors has not been established, but their presence raises the possibility that even selective beta2-agonists may have cardiac effects.

The pharmacologic effects of beta2-adrenoceptor agonist drugs, including salmeterol, are at least in part attributable to stimulation of intracellular adenyl cyclase, the enzyme that catalyzes the conversion of adenosine triphosphate (ATP) to cyclic-3′,5′-adenosine monophosphate (cyclic AMP). Increased cyclic AMP levels cause relaxation of bronchial smooth muscle and inhibition of release of mediators of immediate hypersensitivity from cells, especially from mast cells.

In vitro tests show that salmeterol is a potent and long-lasting inhibitor of the release of mast cell mediators, such as histamine, leukotrienes, and prostaglandin D2, from human lung. Salmeterol inhibits histamine-induced plasma protein extravasation and inhibits platelet-activating factor-induced eosinophil accumulation in the lungs of guinea pigs when administered by the inhaled route. In humans, single doses of salmeterol administered via inhalation aerosol attenuate allergen-induced bronchial hyper-responsiveness.

12.2 Pharmacodynamics

ADVAIR DISKUS

Healthy Subjects: Cardiovascular Effects: Since systemic pharmacodynamic effects of salmeterol are not normally seen at the therapeutic dose, higher doses were used to produce measurable effects. Four (4) trials were conducted with healthy adult subjects: (1) a single-dose crossover trial using 2 inhalations of ADVAIR DISKUS 500/50, fluticasone propionate inhalation powder 500 mcg and salmeterol inhalation powder 50 mcg given concurrently, or fluticasone propionate inhalation powder 500 mcg given alone, (2) a cumulative-dose trial using 50 to 400 mcg of salmeterol inhalation powder given alone or as ADVAIR DISKUS 500/50, (3) a repeat-dose trial for 11 days using 2 inhalations twice daily of ADVAIR DISKUS 250/50, fluticasone propionate inhalation powder 250 mcg, or salmeterol inhalation powder 50 mcg, and (4) a single-dose trial using 5 inhalations of ADVAIR DISKUS 100/50, fluticasone propionate inhalation powder 100 mcg alone, or placebo. In these trials no significant differences were observed in the pharmacodynamic effects of salmeterol (pulse rate, blood pressure, QTc interval, potassium, and glucose) whether the salmeterol was given as ADVAIR DISKUS, concurrently with fluticasone propionate from separate inhalers, or as salmeterol alone. The systemic pharmacodynamic effects of salmeterol were not altered by the presence of fluticasone propionate in ADVAIR DISKUS. The potential effect of salmeterol on the effects of fluticasone propionate on the HPA axis was also evaluated in these trials.

Hypothalamic-Pituitary-Adrenal Axis Effects: No significant differences across treatments were observed in 24-hour urinary cortisol excretion and, where measured, 24-hour plasma cortisol AUC. The systemic pharmacodynamic effects of fluticasone propionate were not altered by the presence of salmeterol in ADVAIR DISKUS in healthy subjects.

Subjects with Asthma: Adult and Adolescent Subjects: Cardiovascular Effects: In clinical trials with ADVAIR DISKUS in adult and adolescent subjects aged 12 years and older with asthma, no significant differences were observed in the systemic pharmacodynamic effects of salmeterol (pulse rate, blood pressure, QTc interval, potassium, and glucose) whether the salmeterol was given alone or as ADVAIR DISKUS. In 72 adult and adolescent subjects with asthma given either ADVAIR DISKUS 100/50 or ADVAIR DISKUS 250/50, continuous 24-hour electrocardiographic monitoring was performed after the first dose and after 12 weeks of therapy, and no clinically significant dysrhythmias were noted.

Hypothalamic-Pituitary-Adrenal Axis Effects: In a 28-week trial in adult and adolescent subjects with asthma, ADVAIR DISKUS 500/50 twice daily was compared with the concurrent use of salmeterol inhalation powder 50 mcg plus fluticasone propionate inhalation powder 500 mcg from separate inhalers or fluticasone propionate inhalation powder 500 mcg alone. No significant differences across treatments were observed in serum cortisol AUC after 12 weeks of dosing or in 24-hour urinary cortisol excretion after 12 and 28 weeks.

In a 12-week trial in adult and adolescent subjects with asthma, ADVAIR DISKUS 250/50 twice daily was compared with fluticasone propionate inhalation powder 250 mcg alone, salmeterol inhalation powder 50 mcg alone, and placebo. For most subjects, the ability to increase cortisol production in response to stress, as assessed by 30-minute cosyntropin stimulation, remained intact with ADVAIR DISKUS. One subject (3%) who received ADVAIR DISKUS 250/50 had an abnormal response (peak serum cortisol <18 mcg/dL) after dosing, compared with 2 subjects (6%) who received placebo, 2 subjects (6%) who received fluticasone propionate 250 mcg, and no subjects who received salmeterol.

In a repeat-dose, 3-way crossover trial, 1 inhalation twice daily of ADVAIR DISKUS 100/50, FLOVENT DISKUS 100 mcg (fluticasone propionate inhalation powder 100 mcg), or placebo was administered to 20 adult and adolescent subjects with asthma. After 28 days of treatment, geometric mean serum cortisol AUC over 12 hours showed no significant difference between ADVAIR DISKUS and FLOVENT DISKUS or between either active treatment and placebo.

Pediatric Subjects: Hypothalamic-Pituitary-Adrenal Axis Effects: In a 12-week trial in subjects with asthma aged 4 to 11 years who were receiving ICS at trial entry, ADVAIR DISKUS 100/50 twice daily was compared with fluticasone propionate inhalation powder 100 mcg administered twice daily via the DISKUS. The values for 24-hour urinary cortisol excretion at trial entry and after 12 weeks of treatment were similar within each treatment group. After 12 weeks, 24-hour urinary cortisol excretion was also similar between the 2 groups.

Subjects with Chronic Obstructive Pulmonary Disease: Cardiovascular Effects: In clinical trials with ADVAIR DISKUS in subjects with COPD, no significant differences were seen in pulse rate, blood pressure, potassium, and glucose between ADVAIR DISKUS, the individual components of ADVAIR DISKUS, and placebo. In a trial of ADVAIR DISKUS 250/50, 8 subjects (2 [1.1%] in the group given ADVAIR DISKUS 250/50, 1 [0.5%] in the fluticasone propionate 250-mcg group, 3 [1.7%] in the salmeterol group, and 2 [1.1%] in the placebo group) had QTc intervals >470 msec at least 1 time during the treatment period. Five (5) of these 8 subjects had a prolonged QTc interval at baseline.

In a 24-week trial, 130 subjects with COPD received continuous 24-hour electrocardiographic monitoring prior to the first dose and after 4 weeks of twice-daily treatment with either ADVAIR DISKUS 500/50, fluticasone propionate inhalation powder 500 mcg, salmeterol inhalation powder 50 mcg, or placebo. No significant differences in ventricular or supraventricular arrhythmias and heart rate were observed among the groups treated with ADVAIR DISKUS 500/50, the individual components, or placebo. One (1) subject in the fluticasone propionate group experienced atrial flutter/atrial fibrillation, and 1 subject in the group given ADVAIR DISKUS 500/50 experienced heart block. There were 3 cases of nonsustained ventricular tachycardia (1 each in the placebo, salmeterol, and fluticasone propionate 500-mcg treatment groups).

In 24-week clinical trials in subjects with COPD, the incidence of clinically significant ECG abnormalities (myocardial ischemia, ventricular hypertrophy, clinically significant conduction abnormalities, clinically significant arrhythmias) was lower for subjects who received salmeterol (1%, 9 of 688 subjects who received either salmeterol 50 mcg or ADVAIR DISKUS) compared with placebo (3%, 10 of 370 subjects).

No significant differences with salmeterol 50 mcg alone or in combination with fluticasone propionate as ADVAIR DISKUS 500/50 were observed on pulse rate and systolic and diastolic blood pressure in a subset of subjects with COPD who underwent 12-hour serial vital sign measurements after the first dose (n = 183) and after 12 weeks of therapy (n = 149). Median changes from baseline in pulse rate and systolic and diastolic blood pressure were similar to those seen with placebo.

Hypothalamic-Pituitary-Adrenal Axis Effects: Short-cosyntropin stimulation testing was performed both at Day 1 and Endpoint in 101 subjects with COPD receiving twice-daily ADVAIR DISKUS 250/50, fluticasone propionate inhalation powder 250 mcg, salmeterol inhalation powder 50 mcg, or placebo. For most subjects, the ability to increase cortisol production in response to stress, as assessed by short cosyntropin stimulation, remained intact with ADVAIR DISKUS 250/50. One (1) subject (3%) who received ADVAIR DISKUS 250/50 had an abnormal stimulated cortisol response (peak cortisol <14.5 mcg/dL assessed by high-performance liquid chromatography) after dosing, compared with 2 subjects (9%) who received fluticasone propionate 250 mcg, 2 subjects (7%) who received salmeterol 50 mcg, and 1 subject (4%) who received placebo following 24 weeks of treatment or early discontinuation from trial.

After 36 weeks of dosing, serum cortisol concentrations in a subset of subjects with COPD (n = 83) were 22% lower in subjects receiving ADVAIR DISKUS 500/50 and 21% lower in subjects receiving fluticasone propionate 500 mcg than in subjects receiving placebo.

Other Fluticasone Propionate Products

Subjects with Asthma: Hypothalamic-Pituitary-Adrenal Axis Effects: In clinical trials with fluticasone propionate inhalation powder using dosages up to and including 250 mcg twice daily, occasional abnormal short cosyntropin tests (peak serum cortisol <18 mcg/dL assessed by radioimmunoassay) were noted both in subjects receiving fluticasone propionate and in subjects receiving placebo. The incidence of abnormal tests at 500 mcg twice daily was greater than placebo. In a 2-year trial carried out with the DISKHALER inhalation device in 64 subjects with mild, persistent asthma (mean FEV1 91% of predicted) randomized to fluticasone propionate 500 mcg twice daily or placebo, no subject receiving fluticasone propionate had an abnormal response to 6-hour cosyntropin infusion (peak serum cortisol <18 mcg/dL). With a peak cortisol threshold of <35 mcg/dL, 1 subject receiving fluticasone propionate (4%) had an abnormal response at 1 year; repeat testing at 18 months and 2 years was normal. Another subject receiving fluticasone propionate (5%) had an abnormal response at 2 years. No subject on placebo had an abnormal response at 1 or 2 years.

Subjects with Chronic Obstructive Pulmonary Disease: Hypothalamic-Pituitary-Adrenal Axis Effects: After 4 weeks of dosing, the steady-state fluticasone propionate pharmacokinetics and serum cortisol levels were described in a subset of subjects with COPD (n = 86) randomized to twice-daily fluticasone propionate inhalation powder via the DISKUS 500 mcg, fluticasone propionate inhalation powder 250 mcg, or placebo. Serial serum cortisol concentrations were measured across a 12-hour dosing interval. Serum cortisol concentrations following 250- and 500-mcg twice-daily dosing were 10% and 21% lower than placebo, respectively, indicating a dose-dependent increase in systemic exposure to fluticasone propionate.

Other Salmeterol Xinafoate Products

Subjects with Asthma: Cardiovascular Effects: Inhaled salmeterol, like other beta-adrenergic agonist drugs, can produce dose-related cardiovascular effects and effects on blood glucose and/or serum potassium [see Warnings and Precautions (5.12, 5.18)]. The cardiovascular effects (heart rate, blood pressure) associated with salmeterol inhalation aerosol occur with similar frequency, and are of similar type and severity, as those noted following albuterol administration.

The effects of rising inhaled doses of salmeterol and standard inhaled doses of albuterol were studied in volunteers and in subjects with asthma. Salmeterol doses up to 84 mcg administered as inhalation aerosol resulted in heart rate increases of 3 to 16 beats/min, about the same as albuterol dosed at 180 mcg by inhalation aerosol (4 to 10 beats/min). Adult and adolescent subjects receiving 50-mcg doses of salmeterol inhalation powder (N = 60) underwent continuous electrocardiographic monitoring during two 12-hour periods after the first dose and after 1 month of therapy, and no clinically significant dysrhythmias were noted.

Concomitant Use of ADVAIR DISKUS with Other Respiratory Medicines

Short-acting Beta2-agonists: In clinical trials in subjects with asthma, the mean daily need for albuterol by 166 adult and adolescent subjects aged 12 years and older using ADVAIR DISKUS was approximately 1.3 inhalations/day and ranged from 0 to 9 inhalations/day. Five percent (5%) of subjects using ADVAIR DISKUS in these trials averaged 6 or more inhalations per day over the course of the 12-week trials. No increase in frequency of cardiovascular adverse events was observed among subjects who averaged 6 or more inhalations per day.

In a clinical trial in subjects with COPD, the mean daily need for albuterol for subjects using ADVAIR DISKUS 250/50 was 4.1 inhalations/day. Twenty-six percent (26%) of subjects using ADVAIR DISKUS 250/50 averaged 6 or more inhalations of albuterol per day over the course of the 24-week trial. No increase in frequency of cardiovascular adverse reactions was observed among subjects who averaged 6 or more inhalations per day.

Methylxanthines: The concurrent use of intravenously or orally administered methylxanthines (e.g., aminophylline, theophylline) by adult and adolescent subjects aged 12 years and older receiving ADVAIR DISKUS has not been completely evaluated. In clinical trials in subjects with asthma, 39 subjects receiving ADVAIR DISKUS 100/50, ADVAIR DISKUS 250/50, or ADVAIR DISKUS 500/50 twice daily concurrently with a theophylline product had adverse event rates similar to those in 304 subjects receiving ADVAIR DISKUS without theophylline. Similar results were observed in subjects receiving salmeterol 50 mcg plus fluticasone propionate 500 mcg twice daily concurrently with a theophylline product (n = 39) or without theophylline (n = 132).

In a clinical trial in subjects with COPD, 17 subjects receiving ADVAIR DISKUS 250/50 twice daily concurrently with a theophylline product had adverse event rates similar to those in 161 subjects receiving ADVAIR DISKUS without theophylline. Based on the available data, the concomitant administration of methylxanthines with ADVAIR DISKUS did not alter the observed adverse event profile.

Fluticasone Propionate Nasal Spray: In adult and adolescent subjects aged 12 years and older receiving ADVAIR DISKUS in clinical trials, no difference in the profile of adverse events or HPA axis effects was noted between subjects who were receiving FLONASE (fluticasone propionate) Nasal Spray, 50 mcg concurrently (n = 46) and those who were not (n = 130).

12.3 Pharmacokinetics

Absorption

Fluticasone Propionate: Healthy Subjects: Fluticasone propionate acts locally in the lung; therefore, plasma levels do not predict therapeutic effect. Trials using oral dosing of labeled and unlabeled drug have demonstrated that the oral systemic bioavailability of fluticasone propionate is negligible (<1%), primarily due to incomplete absorption and presystemic metabolism in the gut and liver. In contrast, the majority of the fluticasone propionate delivered to the lung is systemically absorbed.

Following administration of ADVAIR DISKUS to healthy adult subjects, peak plasma concentrations of fluticasone propionate were achieved in 1 to 2 hours. In a single-dose crossover trial, a higher-than-recommended dose of ADVAIR DISKUS was administered to 14 healthy adult subjects. Two (2) inhalations of the following treatments were administered: ADVAIR DISKUS 500/50, fluticasone propionate inhalation powder 500 mcg and salmeterol inhalation powder 50 mcg given concurrently, and fluticasone propionate inhalation powder 500 mcg alone. Mean peak plasma concentrations of fluticasone propionate averaged 107, 94, and 120 pg/mL, respectively, indicating no significant changes in systemic exposures of fluticasone propionate.

In 15 healthy subjects, systemic exposure to fluticasone propionate from 4 inhalations of ADVAIR HFA 230/21 (fluticasone propionate 230 mcg and salmeterol 21 mcg) Inhalation Aerosol (920/84 mcg) and 2 inhalations of ADVAIR DISKUS 500/50 (1,000/100 mcg) was similar between the 2 inhalers (i.e., 799 versus 832 pg•h/mL, respectively), but approximately half the systemic exposure from 4 inhalations of fluticasone propionate CFC inhalation aerosol 220 mcg (880 mcg, AUC = 1,543 pg•h/mL). Similar results were observed for peak fluticasone propionate plasma concentrations (186 and 182 pg/mL from ADVAIR HFA and ADVAIR DISKUS, respectively, and 307 pg/mL from the fluticasone propionate CFC inhalation aerosol). Absolute bioavailability of fluticasone propionate was 5.3% and 5.5% following administration of ADVAIR HFA and ADVAIR DISKUS, respectively.

Subjects with Asthma and COPD: Peak steady-state fluticasone propionate plasma concentrations in adult subjects with asthma (N = 11) ranged from undetectable to 266 pg/mL after a 500-mcg twice-daily dose of fluticasone propionate inhalation powder using the DISKUS inhaler. The mean fluticasone propionate plasma concentration was 110 pg/mL.

Full pharmacokinetic profiles were obtained from 9 female and 16 male subjects with asthma given fluticasone propionate inhalation powder 500 mcg twice daily using the DISKUS inhaler and from 14 female and 43 male subjects with COPD given 250 or 500 mcg twice daily. No overall differences in fluticasone propionate pharmacokinetics were observed.

Peak steady-state fluticasone propionate plasma concentrations in subjects with COPD averaged 53 pg/mL (range: 19.3 to 159.3 pg/mL) after treatment with 250 mcg twice daily (n = 30) and 84 pg/mL (range: 24.3 to 197.1 pg/mL) after treatment with 500 mcg twice daily (n = 27) via the fluticasone propionate DISKUS inhaler. In another trial in subjects with COPD, peak steady-state fluticasone propionate plasma concentrations averaged 115 pg/mL (range: 52.6 to 366.0 pg/mL) after treatment with 500 mcg twice daily via the fluticasone propionate DISKUS inhaler (n = 15) and 105 pg/mL (range: 22.5 to 299.0 pg/mL) via ADVAIR DISKUS (n = 24).

Salmeterol Xinafoate: Healthy Subjects: Salmeterol xinafoate, an ionic salt, dissociates in solution so that the salmeterol and 1-hydroxy-2-naphthoic acid (xinafoate) moieties are absorbed, distributed, metabolized, and eliminated independently. Salmeterol acts locally in the lung; therefore, plasma levels do not predict therapeutic effect.

Following administration of ADVAIR DISKUS to healthy adult subjects, peak plasma concentrations of salmeterol were achieved in about 5 minutes.

In 15 healthy subjects receiving ADVAIR HFA 230/21 Inhalation Aerosol (920/84 mcg) and ADVAIR DISKUS 500/50 (1,000/100 mcg), systemic exposure to salmeterol was higher (317 versus 169 pg•h/mL) and peak salmeterol concentrations were lower (196 versus 223 pg/mL) following ADVAIR HFA compared with ADVAIR DISKUS, although pharmacodynamic results were comparable.

Subjects with Asthma: Because of the small therapeutic dose, systemic levels of salmeterol are low or undetectable after inhalation of recommended dosages (50 mcg of salmeterol inhalation powder twice daily). Following chronic administration of an inhaled dose of 50 mcg of salmeterol inhalation powder twice daily, salmeterol was detected in plasma within 5 to 45 minutes in 7 subjects with asthma; plasma concentrations were very low, with mean peak concentrations of 167 pg/mL at 20 minutes and no accumulation with repeated doses.

Distribution

Fluticasone Propionate: Following intravenous administration, the initial disposition phase for fluticasone propionate was rapid and consistent with its high lipid solubility and tissue binding. The volume of distribution averaged 4.2 L/kg.

The percentage of fluticasone propionate bound to human plasma proteins averages 99%. Fluticasone propionate is weakly and reversibly bound to erythrocytes and is not significantly bound to human transcortin.

Salmeterol: The percentage of salmeterol bound to human plasma proteins averages 96% in vitro over the concentration range of 8 to 7,722 ng of salmeterol base per milliliter, much higher concentrations than those achieved following therapeutic doses of salmeterol.

Metabolism

Fluticasone Propionate: The total clearance of fluticasone propionate is high (average, 1,093 mL/min), with renal clearance accounting for <0.02% of the total. The only circulating metabolite detected in man is the 17β-carboxylic acid derivative of fluticasone propionate, which is formed through the CYP3A4 pathway. This metabolite had less affinity (approximately 1/2,000) than the parent drug for the glucocorticoid receptor of human lung cytosol in vitro and negligible pharmacological activity in animal studies. Other metabolites detected in vitro using cultured human hepatoma cells have not been detected in man.

Salmeterol: Salmeterol base is extensively metabolized by hydroxylation, with subsequent elimination predominantly in the feces. No significant amount of unchanged salmeterol base was detected in either urine or feces.

An in vitro study using human liver microsomes showed that salmeterol is extensively metabolized to α-hydroxysalmeterol (aliphatic oxidation) by CYP3A4. Ketoconazole, a strong inhibitor of CYP3A4, essentially completely inhibited the formation of α-hydroxysalmeterol in vitro.

Elimination

Fluticasone Propionate: Following intravenous dosing, fluticasone propionate showed polyexponential kinetics and had a terminal elimination half-life of approximately 7.8 hours. Less than 5% of a radiolabeled oral dose was excreted in the urine as metabolites, with the remainder excreted in the feces as parent drug and metabolites. Terminal half-life estimates of fluticasone propionate for ADVAIR HFA, ADVAIR DISKUS, and fluticasone propionate CFC inhalation aerosol were similar and averaged 5.6 hours.

Salmeterol: In 2 healthy adult subjects who received 1 mg of radiolabeled salmeterol (as salmeterol xinafoate) orally, approximately 25% and 60% of the radiolabeled salmeterol was eliminated in urine and feces, respectively, over a period of 7 days. The terminal elimination half-life was about 5.5 hours (1 volunteer only).

The xinafoate moiety has no apparent pharmacologic activity. The xinafoate moiety is highly protein bound (>99%) and has a long elimination half-life of 11 days. No terminal half-life estimates were calculated for salmeterol following administration of ADVAIR DISKUS.

Specific Populations

A population pharmacokinetic analysis was performed for fluticasone propionate and salmeterol utilizing data from 9 controlled clinical trials that included 350 subjects with asthma aged 4 to 77 years who received treatment with ADVAIR DISKUS, the combination of HFA-propelled fluticasone propionate and salmeterol inhalation aerosol (ADVAIR HFA), fluticasone propionate inhalation powder (FLOVENT DISKUS), HFA-propelled fluticasone propionate inhalation aerosol (FLOVENT HFA), or CFC-propelled fluticasone propionate inhalation aerosol. The population pharmacokinetic analyses for fluticasone propionate and salmeterol showed no clinically relevant effects of age, gender, race, body weight, body mass index, or percent of predicted FEV1 on apparent clearance and apparent volume of distribution.

Age: When the population pharmacokinetic analysis for fluticasone propionate was divided into subgroups based on fluticasone propionate strength, formulation, and age (adolescents/adults and children), there were some differences in fluticasone propionate exposure. Higher fluticasone propionate exposure from ADVAIR DISKUS 100/50 compared with FLOVENT DISKUS 100 mcg was observed in adolescents and adults (ratio 1.52 [90% CI: 1.08, 2.13]). However, in clinical trials of up to 12 weeks’ duration comparing ADVAIR DISKUS 100/50 and FLOVENT DISKUS 100 mcg in adolescents and adults, no differences in systemic effects of corticosteroid treatment (e.g., HPA axis effects) were observed. Similar fluticasone propionate exposure was observed from ADVAIR DISKUS 500/50 and FLOVENT DISKUS 500 mcg (ratio 0.83 [90% CI: 0.65, 1.07]) in adolescents and adults.

Steady-state systemic exposure to salmeterol when delivered as ADVAIR DISKUS 100/50, ADVAIR DISKUS 250/50, or ADVAIR HFA 115/21 (fluticasone propionate 115 mcg and salmeterol 21 mcg) Inhalation Aerosol was evaluated in 127 subjects aged 4 to 57 years. The geometric mean AUC was 325 pg•h/mL (90% CI: 309, 341) in adolescents and adults.

The population pharmacokinetic analysis included 160 subjects with asthma aged 4 to 11 years who received ADVAIR DISKUS 100/50 or FLOVENT DISKUS 100 mcg. Higher fluticasone propionate exposure (AUC) was observed in children from ADVAIR DISKUS 100/50 compared with FLOVENT DISKUS 100 mcg (ratio 1.20 [90% CI: 1.06, 1.37]). Higher fluticasone propionate exposure (AUC) from ADVAIR DISKUS 100/50 was observed in children compared with adolescents and adults (ratio 1.63 [90% CI: 1.35, 1.96]). However, in clinical trials of up to 12 weeks’ duration comparing ADVAIR DISKUS 100/50 and FLOVENT DISKUS 100 mcg in both adolescents and adults and in children, no differences in systemic effects of corticosteroid treatment (e.g., HPA axis effects) were observed.

Exposure to salmeterol was higher in children compared with adolescents and adults who received ADVAIR DISKUS 100/50 (ratio 1.23 [90% CI: 1.10, 1.38]). However, in clinical trials of up to 12 weeks’ duration with ADVAIR DISKUS 100/50 in both adolescents and adults and in children, no differences in systemic effects of beta2-agonist treatment (e.g., cardiovascular effects, tremor) were observed.

Male and Female Patients: The population pharmacokinetic analysis involved 202 males and 148 females with asthma who received fluticasone propionate alone or in combination with salmeterol and showed no gender differences for fluticasone propionate pharmacokinetics.

The population pharmacokinetic analysis involved 76 males and 51 females with asthma who received salmeterol in combination with fluticasone propionate and showed no gender differences for salmeterol pharmacokinetics.

Patients with Hepatic and Renal Impairment: Formal pharmacokinetic studies using ADVAIR DISKUS have not been conducted in patients with hepatic or renal impairment. However, since both fluticasone propionate and salmeterol are predominantly cleared by hepatic metabolism, impairment of liver function may lead to accumulation of fluticasone propionate and salmeterol in plasma. Therefore, patients with hepatic disease should be closely monitored.

Drug Interaction Studies

In the repeat- and single-dose trials, there was no evidence of significant drug interaction in systemic exposure between fluticasone propionate and salmeterol when given alone or in combination via the DISKUS. The population pharmacokinetic analysis from 9 controlled clinical trials in 350 subjects with asthma showed no significant effects on fluticasone propionate or salmeterol pharmacokinetics following co-administration with beta2-agonists, corticosteroids, antihistamines, or theophyllines.

Inhibitors of Cytochrome P450 3A4: Ritonavir: Fluticasone Propionate: Fluticasone propionate is a substrate of CYP3A4. Coadministration of fluticasone propionate and the strong CYP3A4 inhibitor ritonavir is not recommended based upon a multiple-dose, crossover drug interaction trial in 18 healthy subjects. Fluticasone propionate aqueous nasal spray (200 mcg once daily) was coadministered for 7 days with ritonavir (100 mg twice daily). Plasma fluticasone propionate concentrations following fluticasone propionate aqueous nasal spray alone were undetectable (<10 pg/mL) in most subjects, and when concentrations were detectable peak levels (Cmax) averaged 11.9 pg/mL (range: 10.8 to 14.1 pg/mL) and AUC(0-τ) averaged 8.43 pg•h/mL (range: 4.2 to 18.8 pg•h/mL). Fluticasone propionate Cmax and AUC(0-τ) increased to 318 pg/mL (range: 110 to 648 pg/mL) and 3,102.6 pg•h/mL (range: 1,207.1 to 5,662.0 pg•h/mL), respectively, after coadministration of ritonavir with fluticasone propionate aqueous nasal spray. This significant increase in plasma fluticasone propionate exposure resulted in a significant decrease (86%) in serum cortisol AUC.

Ketoconazole: Fluticasone Propionate: In a placebo-controlled crossover trial in 8 healthy adult volunteers, coadministration of a single dose of orally inhaled fluticasone propionate (1,000 mcg) with multiple doses of ketoconazole (200 mg) to steady state resulted in increased plasma fluticasone propionate exposure, a reduction in plasma cortisol AUC, and no effect on urinary excretion of cortisol.

Salmeterol: In a placebo-controlled, crossover drug interaction trial in 20 healthy male and female subjects, coadministration of salmeterol (50 mcg twice daily) and the strong CYP3A4 inhibitor ketoconazole (400 mg once daily) for 7 days resulted in a significant increase in plasma salmeterol exposure as determined by a 16-fold increase in AUC (ratio with and without ketoconazole 15.76 [90% CI: 10.66, 23.31]) mainly due to increased bioavailability of the swallowed portion of the dose. Peak plasma salmeterol concentrations were increased by 1.4-fold (90% CI: 1.23, 1.68). Three (3) out of 20 subjects (15%) were withdrawn from salmeterol and ketoconazole coadministration due to beta-agonist–mediated systemic effects (2 with QTc prolongation and 1 with palpitations and sinus tachycardia). Coadministration of salmeterol and ketoconazole did not result in a clinically significant effect on mean heart rate, mean blood potassium, or mean blood glucose. Although there was no statistical effect on the mean QTc, coadministration of salmeterol and ketoconazole was associated with more frequent increases in QTc duration compared with salmeterol and placebo administration.

Erythromycin: Fluticasone Propionate: In a multiple-dose drug interaction trial, coadministration of orally inhaled fluticasone propionate (500 mcg twice daily) and erythromycin (333 mg 3 times daily) did not affect fluticasone propionate pharmacokinetics.

Salmeterol: In a repeat-dose trial in 13 healthy subjects, concomitant administration of erythromycin (a moderate CYP3A4 inhibitor) and salmeterol inhalation aerosol resulted in a 40% increase in salmeterol Cmax at steady state (ratio with and without erythromycin 1.4 [90% CI: 0.96, 2.03], P = 0.12), a 3.6-beat/min increase in heart rate ([95% CI: 0.19, 7.03], P<0.04), a 5.8-msec increase in QTc interval ([95% CI: -6.14, 17.77], P = 0.34), and no change in plasma potassium.

13 NONCLINICAL TOXICOLOGY

13.1 Carcinogenesis, Mutagenesis, Impairment of Fertility

Fluticasone Propionate

Fluticasone propionate demonstrated no tumorigenic potential in mice at oral doses up to 1,000 mcg/kg (approximately 5 and 10 times the MRHDID for adults and children, respectively, on a mcg/m^2 basis) for 78 weeks or in rats at inhalation doses up to 57 mcg/kg (less than and approximately equivalent to the MRHDID for adults and children, respectively, on a mcg/m^2 basis) for 104 weeks.

Fluticasone propionate did not induce gene mutation in prokaryotic or eukaryotic cells in vitro. No significant clastogenic effect was seen in cultured human peripheral lymphocytes in vitro or in the in vivo mouse micronucleus test.

Fertility and reproductive performance were unaffected in male and female rats at subcutaneous doses up to 50 mcg/kg (approximately 0.5 times the MRHDID for adults on a mcg/m^2 basis).

Salmeterol

In an 18-month carcinogenicity study in CD-mice, salmeterol at oral doses of 1,400 mcg/kg and above (approximately 20 times the MRHDID for adults and children based on comparison of the plasma AUCs) caused a dose-related increase in the incidence of smooth muscle hyperplasia, cystic glandular hyperplasia, leiomyomas of the uterus, and ovarian cysts. No tumors were seen at 200 mcg/kg (approximately 3 times the MRHDID for adults and children based on comparison of the AUCs).

In a 24-month oral and inhalation carcinogenicity study in Sprague Dawley rats, salmeterol caused a dose-related increase in the incidence of mesovarian leiomyomas and ovarian cysts at doses of 680 mcg/kg and above (approximately 66 and 35 times the MRHDID for adults and children, respectively, on a mcg/m^2 basis). No tumors were seen at 210 mcg/kg (approximately 20 and 10 times the MRHDID for adults and children, respectively, on a mcg/m^2 basis). These findings in rodents are similar to those reported previously for other beta-adrenergic agonist drugs. The relevance of these findings to human use is unknown.

Salmeterol produced no detectable or reproducible increases in microbial and mammalian gene mutation in vitro. No clastogenic activity occurred in vitro in human lymphocytes or in vivo in a rat micronucleus test.

Fertility and reproductive performance were unaffected in male and female rats at oral doses up to 2,000 mcg/kg (approximately 195 times the MRHDID for adults on a mcg/m^2 basis).

13.2 Animal Toxicology and/or Pharmacology

Preclinical

Studies in laboratory animals (minipigs, rodents, and dogs) have demonstrated the occurrence of cardiac arrhythmias and sudden death (with histologic evidence of myocardial necrosis) when beta-agonists and methylxanthines are administered concurrently. The clinical relevance of these findings is unknown.

14 CLINICAL STUDIES

14.1 Asthma

Adult and Adolescent Subjects Aged 12 Years and Older

In clinical trials comparing ADVAIR DISKUS with its individual components, improvements in most efficacy endpoints were greater with ADVAIR DISKUS than with the use of either fluticasone propionate or salmeterol alone. In addition, clinical trials showed similar results between ADVAIR DISKUS and the concurrent use of fluticasone propionate plus salmeterol at corresponding doses from separate inhalers.

Trials Comparing ADVAIR DISKUS with Fluticasone Propionate Alone or Salmeterol Alone: Three (3) double-blind, parallel-group clinical trials were conducted with ADVAIR DISKUS in 1,208 adult and adolescent subjects (aged 12 years and older, baseline FEV1 63% to 72% of predicted normal) with asthma that was not optimally controlled on their current therapy. All treatments were inhalation powders given as 1 inhalation from the DISKUS inhaler twice daily, and other maintenance therapies were discontinued.

Trial 1: Clinical Trial with ADVAIR DISKUS 100/50: This placebo-controlled, 12-week, U.S. trial compared ADVAIR DISKUS 100/50 with its individual components, fluticasone propionate 100 mcg and salmeterol 50 mcg. The trial was stratified according to baseline asthma maintenance therapy; subjects were using either ICS (n = 250) (daily doses of beclomethasone dipropionate 252 to 420 mcg; flunisolide 1,000 mcg; fluticasone propionate inhalation aerosol 176 mcg; or triamcinolone acetonide 600 to 1,000 mcg) or salmeterol (n = 106). Baseline FEV1 measurements were similar across treatments: ADVAIR DISKUS 100/50, 2.17 L; fluticasone propionate 100 mcg, 2.11 L; salmeterol, 2.13 L; and placebo, 2.15 L.

Predefined withdrawal criteria for lack of efficacy, an indicator of worsening asthma, were utilized for this placebo-controlled trial. Worsening asthma was defined as a clinically important decrease in FEV1 or PEF, increase in use of VENTOLIN (albuterol, USP) Inhalation Aerosol, increase in night awakenings due to asthma, emergency intervention or hospitalization due to asthma, or requirement for asthma medication not allowed by the protocol. As shown in Table 4, statistically significantly fewer subjects receiving ADVAIR DISKUS 100/50 were withdrawn due to worsening asthma compared with fluticasone propionate, salmeterol, and placebo.

Table 4. Percent of Subjects Withdrawn due to Worsening Asthma in Subjects Previously Treated with Either Inhaled Corticosteroids or Salmeterol (Trial 1)
ADVAIR DISKUS; 100/50; (n = 87) | Fluticasone Propionate; 100 mcg; (n = 85) | Salmeterol; 50 mcg; (n = 86) | Placebo; (n = 77)
3% | 11% | 35% | 49%

The FEV1 results are displayed in Figure 1. Because this trial used predetermined criteria for worsening asthma, which caused more subjects in the placebo group to be withdrawn, FEV1 results at Endpoint (last available FEV1 result) are also provided. Subjects receiving ADVAIR DISKUS 100/50 had significantly greater improvements in FEV1 (0.51 L, 25%) compared with fluticasone propionate 100 mcg (0.28 L, 15%), salmeterol (0.11 L, 5%), and placebo (0.01 L, 1%). These improvements in FEV1 with ADVAIR DISKUS were achieved regardless of baseline asthma maintenance therapy (ICS or salmeterol).

Figure 1. Mean Percent Change from Baseline in FEV1 in Subjects with Asthma Previously Treated with Either Inhaled Corticosteroids or Salmeterol (Trial 1)

The effect of ADVAIR DISKUS 100/50 on morning and evening PEF endpoints is shown in Table 5.

Table 5. Peak Expiratory Flow Results for Subjects with Asthma Previously Treated with Either Inhaled Corticosteroids or Salmeterol (Trial 1)
Efficacy Variablea | ADVAIR DISKUS 100/50; (n = 87) | Fluticasone Propionate; 100 mcg; (n = 85) | Salmeterol; 50 mcg; (n = 86) | Placebo; (n = 77)
AM PEF (L/min)
Baseline | 393 | 374 | 369 | 382
Change from baseline | 53 | 17 | -2 | -24
PM PEF (L/min)
Baseline | 418 | 390 | 396 | 398
Change from baseline | 35 | 18 | -7 | -13
AM PEF = morning peak expiratory flow, PM PEF = evening peak expiratory flow.
a Change from baseline = change from baseline at Endpoint (last available data).

The subjective impact of asthma on subjects’ perception of health was evaluated through use of an instrument called the Asthma Quality of Life Questionnaire (AQLQ) (based on a 7-point scale where 1 = maximum impairment and 7 = none). Subjects receiving ADVAIR DISKUS 100/50 had clinically meaningful improvements in overall asthma-specific quality of life as defined by a difference between groups of ≥0.5 points in change from baseline AQLQ scores (difference in AQLQ score of 1.25 compared with placebo).

Trial 2: Clinical Trial with ADVAIR DISKUS 250/50: This placebo-controlled, 12-week, U.S. trial compared ADVAIR DISKUS 250/50 with its individual components, fluticasone propionate 250 mcg and salmeterol 50 mcg, in 349 subjects with asthma using ICS (daily doses of beclomethasone dipropionate 462 to 672 mcg; flunisolide 1,250 to 2,000 mcg; fluticasone propionate inhalation aerosol 440 mcg; or triamcinolone acetonide 1,100 to 1,600 mcg). Baseline FEV1 measurements were similar across treatments: ADVAIR DISKUS 250/50, 2.23 L; fluticasone propionate 250 mcg, 2.12 L; salmeterol, 2.20 L; and placebo, 2.19 L.

Efficacy results in this trial were similar to those observed in Trial 1. Subjects receiving ADVAIR DISKUS 250/50 had significantly greater improvements in FEV1 (0.48 L, 23%) compared with fluticasone propionate 250 mcg (0.25 L, 13%), salmeterol (0.05 L, 4%), and placebo (decrease of 0.11 L, decrease of 5%). Statistically significantly fewer subjects receiving ADVAIR DISKUS 250/50 were withdrawn from this trial for worsening asthma (4%) compared with fluticasone propionate (22%), salmeterol (38%), and placebo (62%). In addition, ADVAIR DISKUS 250/50 was superior to fluticasone propionate, salmeterol, and placebo for improvements in morning and evening PEF. Subjects receiving ADVAIR DISKUS 250/50 also had clinically meaningful improvements in overall asthma-specific quality of life as described in Trial 1 (difference in AQLQ score of 1.29 compared with placebo).

Trial 3: Clinical Trial with ADVAIR DISKUS 500/50: This 28-week, non-U.S. trial compared ADVAIR DISKUS 500/50 with fluticasone propionate 500 mcg alone and concurrent therapy (salmeterol 50 mcg plus fluticasone propionate 500 mcg administered from separate inhalers) twice daily in 503 subjects with asthma using ICS (daily doses of beclomethasone dipropionate 1,260 to 1,680 mcg; budesonide 1,500 to 2,000 mcg; flunisolide 1,500 to 2,000 mcg; or fluticasone propionate inhalation aerosol 660 to 880 mcg [750 to 1,000 mcg inhalation powder]). The primary efficacy parameter, morning PEF, was collected daily for the first 12 weeks of the trial. The primary purpose of weeks 13 to 28 was to collect safety data.

Baseline PEF measurements were similar across treatments: ADVAIR DISKUS 500/50, 359 L/min; fluticasone propionate 500 mcg, 351 L/min; and concurrent therapy, 345 L/min. Morning PEF improved significantly with ADVAIR DISKUS 500/50 compared with fluticasone propionate 500 mcg over the 12-week treatment period. Improvements in morning PEF observed with ADVAIR DISKUS 500/50 were similar to improvements observed with concurrent therapy.

Onset of Action and Progression of Improvement in Asthma Control: The onset of action and progression of improvement in asthma control were evaluated in the 2 placebo-controlled U.S. trials. Following the first dose, the median time to onset of clinically significant bronchodilatation (≥15% improvement in FEV1) in most subjects was seen within 30 to 60 minutes. Maximum improvement in FEV1 generally occurred within 3 hours, and clinically significant improvement was maintained for 12 hours (Figure 2). Following the initial dose, predose FEV1 relative to Day 1 baseline improved markedly over the first week of treatment and continued to improve over the 12 weeks of treatment in both trials. No diminution in the 12-hour bronchodilator effect was observed with either ADVAIR DISKUS 100/50 (Figures 2 and 3) or ADVAIR DISKUS 250/50 as assessed by FEV1 following 12 weeks of therapy.

Figure 2. Percent Change in Serial 12-Hour FEV1 in Subjects with Asthma Previously Using Either Inhaled Corticosteroids or Salmeterol (Trial 1)

First Treatment Day

Figure 3. Percent Change in Serial 12-Hour FEV1 in Subjects with Asthma Previously Using Either Inhaled Corticosteroids or Salmeterol (Trial 1)

Last Treatment Day (Week 12)

Reduction in asthma symptoms and use of rescue VENTOLIN Inhalation Aerosol and improvement in morning and evening PEF also occurred within the first day of treatment with ADVAIR DISKUS, and continued to improve over the 12 weeks of therapy in both trials.

Pediatric Subjects

In a 12-week U.S. trial, ADVAIR DISKUS 100/50 twice daily was compared with fluticasone propionate inhalation powder 100 mcg twice daily in 203 children with asthma aged 4 to 11 years. At trial entry, the children were symptomatic on low doses of ICS (beclomethasone dipropionate 252 to 336 mcg/day; budesonide 200 to 400 mcg/day; flunisolide 1,000 mcg/day; triamcinolone acetonide 600 to 1,000 mcg/day; or fluticasone propionate 88 to 250 mcg/day). The primary objective of this trial was to determine the safety of ADVAIR DISKUS 100/50 compared with fluticasone propionate inhalation powder 100 mcg in this age group; however, the trial also included secondary efficacy measures of pulmonary function. Morning predose FEV1 was obtained at baseline and Endpoint (last available FEV1 result) in children aged 6 to 11 years. In subjects receiving ADVAIR DISKUS 100/50, FEV1 increased from 1.70 L at baseline (n = 79) to 1.88 L at Endpoint (n = 69) compared with an increase from 1.65 L at baseline (n = 83) to 1.77 L at Endpoint (n = 75) in subjects receiving fluticasone propionate 100 mcg.

The findings of this trial, along with extrapolation of efficacy data from subjects aged 12 years and older, support the overall conclusion that ADVAIR DISKUS 100/50 is efficacious in the treatment of asthma in subjects aged 4 to 11 years.

Safety and Efficacy Trials Comparing ADVAIR DISKUS with Fluticasone Propionate

Serious Asthma-Related Events: Two 26-week, randomized, double-blind, parallel-group, active comparator trials were conducted to compare the safety and efficacy of ADVAIR DISKUS with fluticasone propionate inhalation powder in adult and adolescent subjects (Trial 4, NCT01475721) and in pediatric subjects aged 4 to 11 years (Trial 5, NCT01462344). The primary safety objective of both trials was to evaluate whether the addition of salmeterol xinafoate to fluticasone propionate therapy (ADVAIR DISKUS) was non-inferior to ICS fluticasone propionate in terms of the risk of a serious asthma-related event (hospitalization, endotracheal intubation, and death). The trials were designed to rule out pre-defined risk margins for serious asthma-related events of 2.0 for Trial 4 and 2.7 for Trial 5. A blinded adjudication committee determined whether events were asthma related.

Trial 4 enrolled subjects with moderate to severe persistent asthma with a history of asthma-related hospitalization or at least 1 asthma exacerbation in the previous year treated with systemic corticosteroids. A total of 11,679 adult and adolescent subjects [5,834 receiving ADVAIR DISKUS 100/50, ADVAIR DISKUS 250/50, or ADVAIR DISKUS 500/50 and 5,845 receiving fluticasone propionate inhalation powder (100, 250, or 500 mcg)] were included. Trial 5 enrolled subjects with a diagnosis of asthma and a history of at least 1 asthma exacerbation in the previous year treated with systemic corticosteroid. A total of 6,208 subjects aged 4 to 11 years [3,107 receiving ADVAIR DISKUS 100/50 or ADVAIR DISKUS 250/50 and 3,101 receiving fluticasone propionate inhalation powder (100 or 250 mcg)] were included. In both trials, subjects with life-threatening asthma were excluded. In Trials 4 and 5, ADVAIR DISKUS was non-inferior to fluticasone propionate in terms of time to first serious asthma-related events based on the pre-specified risk margins, with estimated hazard ratios of 1.03 (95% CI: 0.64, 1.66) and 1.29 (95% CI: 0.73, 2.27), respectively (Table 6).

Table 6. Serious Asthma-Related Events in the 26-Week Trials 4 and 5
 | Adult and Adolescent Subjects Aged 12 Years and Older (Trial 4) |  | Pediatric Subjects Aged 4 to 11 Years (Trial 5)
 | ADVAIR DISKUS; (n = 5,834) | Fluticasone Propionate Inhalation Powder; (n = 5,845) | ADVAIR DISKUS; (n = 3,107) | Fluticasone Propionate Inhalation Powder; (n = 3,101)
Serious asthma-related event (hospitalization, endotracheal intubation, and death)a | 34 (0.6%) | 33 (0.6%) | 27 (0.9%) | 21 (0.7%)
Hazard ratio (ADVAIR DISKUS/fluticasone propionate) | 1.03; (0.64-1.66)b |  | 1.29; (0.73-2.27)b
Asthma-related death | 0 | 0 | 0 | 0
Asthma-related intubation (endotracheal) | 0 | 2 | 0 | 0
Asthma-related hospitalization (≥24-hour stay) | 34 | 33 | 27 | 21
a Number of subjects with event that occurred within 6 months after the first use of study drug or 7 days after the last date of study drug treatment, whichever date was later. Subjects can have one or more events, but only the first event was counted for analysis. A blinded adjudication committee determined whether events were asthma related.
b The hazard ratio for time to first event was based on a Cox proportional hazards model with a single covariate of treatment (ADVAIR DISKUS vs. fluticasone propionate) and baseline hazards stratified by incoming asthma medication/asthma control status. If the resulting upper 95% CI estimate for the relative risk was <2.0 (Trial 4) or <2.7 (Trial 5), then non-inferiority was concluded.

Effect on Exacerbation: Trials 4 and 5 included time to first exacerbation as a secondary endpoint, where exacerbation was defined as a deterioration of asthma requiring the use of systemic corticosteroids for at least 3 days or an in-patient hospitalization or emergency department visit due to asthma that required systemic corticosteroids. In Trials 4 and 5, the hazard ratio for the time to first asthma exacerbation for ADVAIR DISKUS relative to fluticasone propionate inhalation powder was 0.79 (95% CI: 0.70, 0.89) and 0.86 (95% CI: 0.73, 1.01), respectively. The difference in exacerbations was primarily driven by a reduction in those requiring systemic corticosteroids only.

14.2 Chronic Obstructive Pulmonary Disease

The efficacy of ADVAIR DISKUS 250/50 and ADVAIR DISKUS 500/50 in the treatment of subjects with COPD was evaluated in 6 randomized, double-blind, parallel-group clinical trials in adult subjects aged 40 years and older. These trials were primarily designed to evaluate the efficacy of ADVAIR DISKUS on lung function (3 trials), exacerbations (2 trials), and survival (1 trial).

Lung Function

Two (2) of the 3 clinical trials primarily designed to evaluate the efficacy of ADVAIR DISKUS on lung function were conducted in 1,414 subjects with COPD associated with chronic bronchitis. In these 2 trials, all the subjects had a history of cough productive of sputum that was not attributable to another disease process on most days for at least 3 months of the year for at least 2 years. The trials were randomized, double-blind, parallel-group, 24-week treatment duration. One (1) trial evaluated the efficacy of ADVAIR DISKUS 250/50 compared with its components fluticasone propionate 250 mcg and salmeterol 50 mcg and with placebo, and the other trial evaluated the efficacy of ADVAIR DISKUS 500/50 compared with its components fluticasone propionate 500 mcg and salmeterol 50 mcg and with placebo. Trial treatments were inhalation powders given as 1 inhalation from the DISKUS inhaler twice daily. Maintenance COPD therapies were discontinued, with the exception of theophylline. The subjects had a mean pre-bronchodilator FEV1 of 41% and 20% reversibility at trial entry. Percent reversibility was calculated as 100 times (FEV1 post-albuterol minus FEV1 pre-albuterol)/FEV1 pre-albuterol.

Improvements in lung function (as defined by predose and postdose FEV1) were significantly greater with ADVAIR DISKUS than with fluticasone propionate, salmeterol, or placebo. The improvement in lung function with ADVAIR DISKUS 500/50 was similar to the improvement seen with ADVAIR DISKUS 250/50.

Figures 4 and 5 display predose and 2-hour postdose, respectively, FEV1 results for the trial with ADVAIR DISKUS 250/50. To account for subject withdrawals during the trial, FEV1 at Endpoint (last evaluable FEV1) was evaluated. Subjects receiving ADVAIR DISKUS 250/50 had significantly greater improvements in predose FEV1 at Endpoint (165 mL, 17%) compared with salmeterol 50 mcg (91 mL, 9%) and placebo (1 mL, 1%), demonstrating the contribution of fluticasone propionate to the improvement in lung function with ADVAIR DISKUS (Figure 4). Subjects receiving ADVAIR DISKUS 250/50 had significantly greater improvements in postdose FEV1 at Endpoint (281 mL, 27%) compared with fluticasone propionate 250 mcg (147 mL, 14%) and placebo (58 mL, 6%), demonstrating the contribution of salmeterol to the improvement in lung function with ADVAIR DISKUS (Figure 5).

Figure 4. Predose FEV1: Mean Percent Change from Baseline in Subjects with Chronic Obstructive Pulmonary Disease

Figure 5. Two-Hour Postdose FEV1: Mean Percent Changes from Baseline over Time in Subjects with Chronic Obstructive Pulmonary Disease

The third trial was a 1-year trial that evaluated ADVAIR DISKUS 500/50, fluticasone propionate 500 mcg, salmeterol 50 mcg, and placebo in 1,465 subjects. The subjects had an established history of COPD and exacerbations, a pre-bronchodilator FEV1 <70% of predicted at trial entry, and 8.3% reversibility. The primary endpoint was the comparison of pre-bronchodilator FEV1 in the groups receiving ADVAIR DISKUS 500/50 or placebo. Subjects treated with ADVAIR DISKUS 500/50 had greater improvements in FEV1 (113 mL, 10%) compared with fluticasone propionate 500 mcg (7 mL, 2%), salmeterol (15 mL, 2%), and placebo (-60 mL, -3%).

Exacerbations

Two (2) trials were primarily designed to evaluate the effect of ADVAIR DISKUS 250/50 on exacerbations. In these 2 trials, exacerbations were defined as worsening of 2 or more major symptoms (dyspnea, sputum volume, and sputum purulence) or worsening of any 1 major symptom together with any 1 of the following minor symptoms: sore throat, colds (nasal discharge and/or nasal congestion), fever without other cause, and increased cough or wheeze for at least 2 consecutive days. COPD exacerbations were considered of moderate severity if treatment with systemic corticosteroids and/or antibiotics was required and were considered severe if hospitalization was required.

Exacerbations were also evaluated as a secondary outcome in the 1- and 3-year trials with ADVAIR DISKUS 500/50. There was not a symptomatic definition of exacerbation in these 2 trials. Exacerbations were defined in terms of severity requiring treatment with antibiotics and/or systemic corticosteroids (moderately severe) or requiring hospitalization (severe).

The 2 exacerbation trials with ADVAIR DISKUS 250/50 were identical trials designed to evaluate the effect of ADVAIR DISKUS 250/50 and salmeterol 50 mcg, each given twice daily, on exacerbations of COPD over a 12-month period. A total of 1,579 subjects had an established history of COPD (but no other significant respiratory disorders). Subjects had a pre-bronchodilator FEV1 of 33% of predicted, a mean reversibility of 23% at baseline, and a history of ≥1 COPD exacerbation in the previous year that was moderate or severe. All subjects were treated with ADVAIR DISKUS 250/50 twice daily during a 4-week run-in period prior to being assigned trial treatment with twice-daily ADVAIR DISKUS 250/50 or salmeterol 50 mcg. In both trials, treatment with ADVAIR DISKUS 250/50 resulted in a significantly lower annual rate of moderate/severe COPD exacerbations compared with salmeterol (30.5% reduction [95% CI: 17.0, 41.8], P<0.001) in the first trial and (30.4% reduction [95% CI: 16.9, 41.7], P<0.001) in the second trial. Subjects treated with ADVAIR DISKUS 250/50 also had a significantly lower annual rate of exacerbations requiring treatment with oral corticosteroids compared with subjects treated with salmeterol (39.7% reduction [95% CI: 22.8, 52.9], P<0.001) in the first trial and (34.3% reduction [95% CI: 18.6, 47.0], P<0.001) in the second trial. Secondary endpoints including pulmonary function and symptom scores improved more in subjects treated with ADVAIR DISKUS 250/50 than with salmeterol 50 mcg in both trials.

Exacerbations were evaluated in the 1- and the 3-year trials with ADVAIR DISKUS 500/50 as 1 of the secondary efficacy endpoints. In the 1-year trial, the group receiving ADVAIR DISKUS 500/50 had a significantly lower rate of moderate and severe exacerbations compared with placebo (25.4% reduction compared with placebo [95% CI: 13.5, 35.7]) but not when compared with its components (7.5% reduction compared with fluticasone propionate [95% CI: -7.3, 20.3] and 7% reduction compared with salmeterol [95% CI: -8.0, 19.9]). In the 3-year trial, the group receiving ADVAIR DISKUS 500/50 had a significantly lower rate of moderate and severe exacerbations compared with each of the other treatment groups (25.1% reduction compared with placebo [95% CI: 18.6, 31.1], 9.0% reduction compared with fluticasone propionate [95% CI: 1.2, 16.2], and 12.2% reduction compared with salmeterol [95% CI: 4.6, 19.2]).

There were no trials conducted to directly compare the efficacy of ADVAIR DISKUS 250/50 with ADVAIR DISKUS 500/50 on exacerbations. Across trials, the reduction in exacerbations seen with ADVAIR DISKUS 500/50 was not greater than the reduction in exacerbations seen with ADVAIR DISKUS 250/50.

Survival

A 3-year multicenter, international trial evaluated the efficacy of ADVAIR DISKUS 500/50 compared with fluticasone propionate 500 mcg, salmeterol 50 mcg, and placebo on survival in 6,112 subjects with COPD. During the trial subjects were permitted usual COPD therapy with the exception of other ICS and long-acting bronchodilators. The subjects were aged 40 to 80 years with an established history of COPD, a pre-bronchodilator FEV1 <60% of predicted at trial entry, and <10% of predicted reversibility. Each subject who withdrew from double-blind treatment for any reason was followed for the full 3-year trial period to determine survival status. The primary efficacy endpoint was all-cause mortality. Survival with ADVAIR DISKUS 500/50 was not significantly improved compared with placebo or the individual components (all-cause mortality rate 12.6% ADVAIR DISKUS versus 15.2% placebo). The rates for all-cause mortality were 13.5% and 16.0% in the groups treated with salmeterol 50 mcg and fluticasone propionate 500 mcg, respectively. Secondary outcomes, including pulmonary function (post-bronchodilator FEV1), improved with ADVAIR DISKUS 500/50, salmeterol 50 mcg, and fluticasone propionate 500 mcg compared with placebo.

16 HOW SUPPLIED/STORAGE AND HANDLING

Product: 50090-0732

NDC: 50090-0732-0 60 POWDER in a INHALER / 1 in a CARTON

17 PATIENT COUNSELING INFORMATION

Advise the patient to read the FDA-approved patient labeling (Patient Information and Instructions for Use).

Serious Asthma-Related Events

Inform patients with asthma that LABA when used alone increases the risk of asthma-related hospitalization or asthma-related death. Available data show that when ICS and LABA are used together, such as with ADVAIR DISKUS, there is not a significant increase in the risk of these events.

Not for Acute Symptoms

Inform patients that ADVAIR DISKUS is not meant to relieve acute asthma symptoms or exacerbations of COPD and extra doses should not be used for that purpose. Advise patients to treat acute symptoms with an inhaled, short-acting beta2-agonist such as albuterol. Provide patients with such medication and instruct them in how it should be used.

Instruct patients to seek medical attention immediately if they experience any of the following:

- Decreasing effectiveness of inhaled, short-acting beta2-agonists
- Need for more inhalations than usual of inhaled, short-acting beta2-agonists
- Significant decrease in lung function as outlined by the physician

Tell patients they should not stop therapy with ADVAIR DISKUS without physician/provider guidance since symptoms may recur after discontinuation.

Do Not Use Additional Long-acting Beta2-agonists

Instruct patients not to use other LABA for asthma and COPD.

Local Effects

Inform patients that localized infections with Candida albicans occurred in the mouth and pharynx in some patients. If oropharyngeal candidiasis develops, treat it with appropriate local or systemic (i.e., oral) antifungal therapy while still continuing therapy with ADVAIR DISKUS, but at times therapy with ADVAIR DISKUS may need to be temporarily interrupted under close medical supervision. Advise patients to rinse the mouth with water without swallowing after inhalation to help reduce the risk of thrush.

Pneumonia

Patients with COPD have a higher risk of pneumonia; instruct them to contact their healthcare providers if they develop symptoms of pneumonia.

Immunosuppression

Warn patients who are on immunosuppressant doses of corticosteroids to avoid exposure to chickenpox or measles and, if exposed, to consult their physicians without delay. Inform patients of potential worsening of existing tuberculosis; fungal, bacterial, viral, or parasitic infections; or ocular herpes simplex.

Hypercorticism and Adrenal Suppression

Advise patients that ADVAIR DISKUS may cause systemic corticosteroid effects of hypercorticism and adrenal suppression. Additionally, inform patients that deaths due to adrenal insufficiency have occurred during and after transfer from systemic corticosteroids. Patients should taper slowly from systemic corticosteroids if transferring to ADVAIR DISKUS.

Immediate Hypersensitivity Reactions

Advise patients that immediate hypersensitivity reactions (e.g., urticaria, angioedema, rash, bronchospasm, hypotension), including anaphylaxis, may occur after administration of ADVAIR DISKUS. Patients should discontinue ADVAIR DISKUS if such reactions occur. There have been reports of anaphylactic reactions in patients with severe milk protein allergy after inhalation of powder products containing lactose; therefore, patients with severe milk protein allergy should not take ADVAIR DISKUS.

Reduction in Bone Mineral Density

Advise patients who are at an increased risk for decreased BMD that the use of corticosteroids may pose an additional risk.

Reduced Growth Velocity

Inform patients that orally inhaled corticosteroids, including fluticasone propionate, may cause a reduction in growth velocity when administered to pediatric patients. Physicians should closely follow the growth of children and adolescents taking corticosteroids by any route.

Glaucoma and Cataracts

Advise patients that long-term use of ICS may increase the risk of some eye problems (cataracts or glaucoma); consider regular eye examinations.

Risks Associated with Beta-agonist Therapy

Inform patients of adverse effects associated with beta2-agonists, such as palpitations, chest pain, rapid heart rate, tremor, or nervousness.

Trademarks are owned by or licensed to the GSK group of companies.

GlaxoSmithKline

Durham, NC 27701

©2023 GSK group of companies or its licensor.

ADD:18PI

PATIENT INFORMATION

ADVAIR DISKUS (AD-vair DISK-us)

(fluticasone propionate and salmeterol inhalation powder)

for oral inhalation use

What is ADVAIR DISKUS?

- ADVAIR DISKUS combines the inhaled corticosteroid (ICS) medicine fluticasone propionate and the long-acting beta2-adrenergic agonist (LABA) medicine salmeterol.
  - ICS medicines such as fluticasone propionate help to decrease inflammation in the lungs. Inflammation in the lungs can lead to breathing problems.
  - LABA medicines such as salmeterol help the muscles around the airways in your lungs stay relaxed to prevent symptoms, such as wheezing, cough, chest tightness, and shortness of breath. These symptoms can happen when the muscles around the airways tighten. This makes it hard to breathe.
- ADVAIR DISKUS is not used to relieve sudden breathing problems and will not replace a rescue inhaler.
- It is not known if ADVAIR DISKUS is safe and effective in children younger than 4 years.
- ADVAIR DISKUS is used for asthma and chronic obstructive pulmonary disease (COPD) as follows:
Asthma:
  1. ADVAIR DISKUS is a prescription medicine used to control symptoms of asthma and to prevent symptoms such as wheezing in adults and children aged 4 years and older.
  2. ADVAIR DISKUS contains salmeterol, the same medicine found in SEREVENT DISKUS (salmeterol xinafoate inhalation powder). LABA medicines such as salmeterol when used alone increase the risk of hospitalizations and death from asthma problems. ADVAIR DISKUS contains an ICS and a LABA. When an ICS and LABA are used together, there is not a significant increased risk in hospitalizations and death from asthma problems.
  3. ADVAIR DISKUS is not for adults and children with asthma who are well controlled with an asthma control medicine, such as a low to medium dose of an ICS medicine. ADVAIR DISKUS is for adults and children with asthma who need both an ICS and LABA medicine.
COPD:
ADVAIR DISKUS 250/50 is a prescription medicine used to treat COPD. COPD is a chronic lung disease that includes chronic bronchitis, emphysema, or both. ADVAIR DISKUS 250/50 is used long term as 1 inhalation 2 times each day to improve symptoms of COPD for better breathing and to reduce the number of flare-ups (the worsening of your COPD symptoms for several days).

Do not use ADVAIR DISKUS:

- to relieve sudden breathing problems.
- as a rescue inhaler.
- if you have a severe allergy to milk proteins. Ask your healthcare provider if you are not sure.
- if you are allergic to fluticasone propionate, salmeterol, or any of the ingredients in ADVAIR DISKUS. See the end of this Patient Information for a complete list of ingredients in ADVAIR DISKUS.

Before using ADVAIR DISKUS, tell your healthcare provider about all of your medical conditions, including if you:

- have heart problems.
- have high blood pressure.
- have seizures.
- have thyroid problems.
- have diabetes.
- have liver problems.
- have weak bones (osteoporosis).
- have an immune system problem.
- have or have had eye problems such as glaucoma, increased pressure in your eye, cataracts, or other changes in vision.
- are allergic to milk proteins.
- have any type of viral, bacterial, or fungal infection.
- are exposed to chickenpox or measles.
- are pregnant or plan to become pregnant. It is not known if ADVAIR DISKUS may harm your unborn baby.
- are breastfeeding. It is not known if the medicines in ADVAIR DISKUS pass into your milk and if they can harm your baby.

Tell your healthcare provider about all the medicines you take, including prescription and over-the-counter medicines, vitamins, and herbal supplements. ADVAIR DISKUS and certain other medicines may interact with each other. This may cause serious side effects. Especially tell your healthcare provider if you take antifungal or anti-HIV medicines.

Know the medicines you take. Keep a list of them to show your healthcare provider and pharmacist when you get a new medicine.

How should I use ADVAIR DISKUS?

Read the step-by-step instructions for using ADVAIR DISKUS at the end of this Patient Information.

- Do not use ADVAIR DISKUS unless your healthcare provider has taught you how to use the inhaler and you understand how to use it correctly.
- Children should use ADVAIR DISKUS with an adult’s help, as instructed by the child’s healthcare provider.
- ADVAIR DISKUS comes in 3 different strengths. Your healthcare provider prescribed the strength that is best for you.
- Use ADVAIR DISKUS exactly as your healthcare provider tells you to use it. Do not use ADVAIR DISKUS more often than prescribed.
- Use 1 inhalation of ADVAIR DISKUS 2 times each day. Use ADVAIR DISKUS at the same time each day, about 12 hours apart.
- If you miss a dose of ADVAIR DISKUS, just skip that dose. Take your next dose at your usual time. Do not take 2 doses at 1 time.
- If you take too much ADVAIR DISKUS, call your healthcare provider or go to the nearest hospital emergency room right away if you have any unusual symptoms, such as worsening shortness of breath, chest pain, increased heart rate, or shakiness.
- Do not use other medicines that contain a LABA for any reason. Ask your healthcare provider or pharmacist if any of your other medicines are LABA medicines.
- Do not stop using ADVAIR DISKUS, even if you are feeling better, unless your healthcare provider tells you to.
- ADVAIR DISKUS does not relieve sudden breathing problems. Always have a rescue inhaler with you to treat sudden symptoms. If you do not have a rescue inhaler, call your healthcare provider to have one prescribed for you.
- Rinse your mouth with water without swallowing after each dose of ADVAIR DISKUS. This will help lessen the chance of getting a yeast infection (thrush) in your mouth and throat.
- Call your healthcare provider or get medical care right away if:
  - your breathing problems get worse.
  - you need to use your rescue inhaler more often than usual.
  - your rescue inhaler does not work as well to relieve your symptoms.
  - you need to use 4 or more inhalations of your rescue inhaler in 24 hours for 2 or more days in a row.
  - you use 1 whole canister of your rescue inhaler in 8 weeks.
  - your peak flow meter results decrease. Your healthcare provider will tell you the numbers that are right for you.
  - you have asthma and your symptoms do not improve after using ADVAIR DISKUS regularly for 1 week.

What are the possible side effects of ADVAIR DISKUS?

ADVAIR DISKUS can cause serious side effects, including:

- fungal infection in your mouth or throat (thrush). Rinse your mouth with water without swallowing after using ADVAIR DISKUS to help reduce your chance of getting thrush.
- pneumonia. People with COPD have a higher chance of getting pneumonia. ADVAIR DISKUS may increase the chance of you getting pneumonia. Call your healthcare provider right away if you have any of the following symptoms:

- increase in mucus (sputum) production
- change in mucus color
- fever

- chills
- increased cough
- increased breathing problems

- weakened immune system and increased chance of getting infections (immunosuppression).
- reduced adrenal function (adrenal insufficiency). Adrenal insufficiency is a condition where the adrenal glands do not make enough steroid hormones. This can happen when you stop taking oral corticosteroid medicines (such as prednisone) and start taking a medicine containing an inhaled steroid (such as ADVAIR DISKUS). During this transition period, when your body is under stress such as from fever, trauma (such as a car accident), infection, surgery, or worse COPD symptoms, adrenal insufficiency can get worse and may cause death.
Symptoms of adrenal insufficiency include:

- feeling tired
- lack of energy
- weakness

- nausea and vomiting
- low blood pressure (hypotension)

- sudden breathing problems immediately after inhaling your medicine. If you have sudden breathing problems immediately after inhaling your medicine, stop using ADVAIR DISKUS and call your healthcare provider right away.
- serious allergic reactions. Call your healthcare provider or get emergency medical care if you get any of the following symptoms of a serious allergic reaction:

- rash
- hives

- swelling of your face, mouth, and tongue
- breathing problems

- effects on heart.

- increased blood pressure
- a fast or irregular heartbeat

- chest pain

- effects on nervous system.

- tremor

- nervousness

- bone thinning or weakness (osteoporosis).
- slowed growth in children. Your child’s growth should be checked regularly by the healthcare provider while using ADVAIR DISKUS.
- eye problems including glaucoma, increased pressure in your eye, cataracts, or other changes in vision. You should have regular eye exams while using ADVAIR DISKUS.
- changes in laboratory blood levels (sugar, potassium, certain types of white blood cells).

Common side effects of ADVAIR DISKUS include:

Asthma:

- upper respiratory tract infection
- throat irritation
- hoarseness and voice changes
- thrush in your mouth or throat. Rinse your mouth with water without swallowing after use to help prevent this.

- bronchitis
- cough
- headache
- nausea and vomiting

In children with asthma, infections in the ear, nose, and throat are common.

COPD:

- thrush in your mouth or throat. Rinse your mouth with water without swallowing after use to help prevent this.
- throat irritation
- hoarseness and voice changes

- viral respiratory infections
- headache
- muscle and bone pain

These are not all the possible side effects of ADVAIR DISKUS.

Call your doctor for medical advice about side effects. You may report side effects to FDA at 1-800-FDA-1088.

How should I store ADVAIR DISKUS?

- Store ADVAIR DISKUS at room temperature between 68°F and 77°F (20°C and 25°C). Keep in a dry place away from heat and sunlight.
- Store ADVAIR DISKUS in the unopened foil pouch and only open when ready for use.
- Safely throw away ADVAIR DISKUS in the trash 1 month after you open the foil pouch or when the counter reads 0, whichever comes first.

Keep ADVAIR DISKUS and all medicines out of the reach of children.

General information about the safe and effective use of ADVAIR DISKUS.

Medicines are sometimes prescribed for purposes other than those listed in a Patient Information leaflet. Do not use ADVAIR DISKUS for a condition for which it was not prescribed. Do not give ADVAIR DISKUS to other people, even if they have the same symptoms that you have. It may harm them.

You can ask your healthcare provider or pharmacist for information about ADVAIR DISKUS that was written for health professionals.

What are the ingredients in ADVAIR DISKUS?

Active ingredients: fluticasone propionate, salmeterol xinafoate

Inactive ingredient: lactose monohydrate (contains milk proteins)

For more information about ADVAIR DISKUS, call 1-888-825-5249.

Trademarks are owned by or licensed to the GSK group of companies.

GlaxoSmithKline, Durham, NC 27701

©2023 GSK group of companies or its licensor.

ADD:14PIL

This Patient Information has been approved by the U.S. Food and Drug Administration. Revised: June 2023

INSTRUCTIONS FOR USE

ADVAIR DISKUS (AD-vair DISK-us)

(fluticasone propionate and salmeterol inhalation powder)

for oral inhalation use

Read this Instructions for Use before you start using ADVAIR DISKUS and each time you get a refill. There may be new information. This information does not take the place of talking to your healthcare provider about your medical condition or treatment.

Your ADVAIR DISKUS inhaler

Figure A

Important information about your ADVAIR DISKUS inhaler:

- ADVAIR DISKUS is for oral inhalation use only.
- Take ADVAIR DISKUS out of the foil pouch just before you use it for the first time. Safely throw away the pouch. The DISKUS will be in the closed position.
- Write the date you opened the foil pouch in the first blank line on the label. See Figure A.
- Write the “use by” date in the second blank line on the label. See Figure A. That date is 1 month after the date you wrote in the first line.
- The counter should read 60. If you have an institutional pack (with “INSTITUTIONAL PACK” on the back label), the counter should read 14.

How to use your ADVAIR DISKUS inhaler

Follow these steps every time you use ADVAIR DISKUS.

Step 1. Open your ADVAIR DISKUS.

- Hold the DISKUS in your left hand and place the thumb of your right hand in the thumb grip. Push the thumb grip away from you as far as it will go until the mouthpiece shows and snaps into place. See Figure B.

Step 2. Slide the lever until you hear it click.

- Hold the DISKUS in a level, flat position with the mouthpiece towards you. Slide the lever away from the mouthpiece as far as it will go until it clicks. See Figure C.

Figure B

Figure C

- The number on the counter will count down by 1. The DISKUS is now ready to use.

Follow the instructions below so you will not accidentally waste a dose:

- Do not close the DISKUS.
- Do not tilt the DISKUS.
- Do not move the lever on the DISKUS.

Step 3. Inhale your medicine.

- Before you breathe in your dose from the DISKUS, breathe out (exhale) as long as you can while you hold the DISKUS level and away from your mouth. See Figure D. Do not breathe into the mouthpiece.
- Put the mouthpiece to your lips. See Figure E. Breathe in quickly and deeply through the DISKUS. Do not breathe in through your nose.

Figure D

Figure E

- Remove the DISKUS from your mouth and hold your breath for about 10 seconds, or for as long as is comfortable for you.
- Breathe out slowly as long as you can. See Figure D.
- The DISKUS delivers your dose of medicine as a very fine powder that you may or may not taste or feel. Do not take an extra dose from the DISKUS even if you do not taste or feel the medicine.

Step 4. Close the DISKUS.

- Place your thumb in the thumb grip and slide it back towards you as far as it will go. See Figure F. Make sure the DISKUS clicks shut and you cannot see the mouthpiece.

Figure F

- The DISKUS is now ready for you to take your next scheduled dose in about 12 hours. When you are ready to take your next dose, repeat Steps 1 through 4.

Step 5. Rinse your mouth.

- Rinse your mouth with water after breathing in the medicine. Spit out the water. Do not swallow it. See Figure G.

Figure G

When should you get a refill?

The counter on top of the DISKUS shows you how many doses are left. After you have taken 55 doses (9 doses from the institutional pack), the numbers 5 to 0 will show in red. See Figure H. These numbers warn you there are only a few doses left and are a reminder to get a refill.

Figure H

For correct use of the DISKUS, remember:

- Always use the DISKUS in a level, flat position.
- Make sure the lever firmly clicks into place.
- Hold your breath for about 10 seconds after inhaling. Then breathe out fully.
- After each dose, rinse your mouth with water and spit it out. Do not swallow the water.
- Do not take an extra dose, even if you did not taste or feel the powder.
- Do not take the DISKUS apart.
- Do not wash the DISKUS.
- Always keep the DISKUS in a dry place.
- Do not use the DISKUS with a spacer device.

For more information about ADVAIR DISKUS or how to use your inhaler, call 1-888-825-5249.

Trademarks are owned by or licensed to the GSK group of companies.

GlaxoSmithKline, Durham, NC 27701

©2023 GSK group of companies or its licensor.

ADD:7IFU

This Instructions for Use has been approved by the U.S. Food and Drug Administration Revised: June 2023

MEDICATION GUIDE

ADVAIR DISKUS® [ ad′ vair disk′ us]

(fluticasone propionate and

salmeterol inhalation powder)

for oral inhalation

What is the most important information I should know about ADVAIR DISKUS?

ADVAIR DISKUS can cause serious side effects, including:

- People with asthma who take long-acting beta2-adrenergic agonist (LABA) medicines, such as salmeterol (one of the medicines in ADVAIR DISKUS), have an increased risk of death from asthma problems. It is not known whether fluticasone propionate, the other medicine in ADVAIR DISKUS, reduces the risk of death from asthma problems seen with LABA medicines.
- It is not known if LABA medicines such as salmeterol increase the risk of death in people with COPD.
- Call your healthcare provider if breathing problems worsen over time while using ADVAIR DISKUS. You may need different treatment.
- Get emergency medical care if:
  - your breathing problems worsen quickly.
  - you use your rescue inhaler, but it does not relieve your breathing problems.
- ADVAIR DISKUS should be used only if your healthcare provider decides that your asthma is not well controlled with a long-term asthma control medicine, such as an inhaled corticosteroid. When your asthma is well controlled, your healthcare provider may tell you to stop taking ADVAIR DISKUS. Your healthcare provider will decide if you can stop ADVAIR DISKUS without loss of asthma control. Your healthcare provider may prescribe a different asthma control medicine for you, such as an inhaled corticosteroid.
- Children and adolescents who take LABA medicines may have an increased risk of being hospitalized for asthma problems.

What is ADVAIR DISKUS?

- ADVAIR DISKUS combines the inhaled corticosteroid (ICS) medicine fluticasone propionate and the LABA medicine salmeterol.
- ICS medicines such as fluticasone propionate help to decrease inflammation in the lungs. Inflammation in the lungs can lead to breathing problems.
- LABA medicines such as salmeterol help the muscles around the airways in your lungs stay relaxed to prevent symptoms, such as wheezing, cough, chest tightness, and shortness of breath. These symptoms can happen when the muscles around the airways tighten. This makes it hard to breathe.
- ADVAIR DISKUS is not used to relieve sudden breathing problems.
- It is not known if ADVAIR DISKUS is safe and effective in children younger than 4 years.
- ADVAIR DISKUS is used for asthma and COPD as follows:
- Asthma:
  1. ADVAIR DISKUS is a prescription medicine used to control symptoms of asthma and to prevent symptoms such as wheezing in adults and children aged 4 years and older.
  2. ADVAIR DISKUS contains salmeterol, the same medicine found in SEREVENT® DISKUS® (salmeterol xinafoate inhalation powder). LABA medicines such as salmeterol increase the risk of death from asthma problems.
  3. ADVAIR DISKUS is not for adults and children with asthma who are well controlled with an asthma control medicine, such as a low to medium dose of an inhaled corticosteroid medicine.
- COPD:
- ADVAIR DISKUS 250/50 is a prescription medicine used to treat COPD. COPD is a chronic lung disease that includes chronic bronchitis, emphysema, or both. ADVAIR DISKUS 250/50 is used long term as 1 inhalation 2 times each day to improve symptoms of COPD for better breathing and to reduce the number of flare-ups (the worsening of your COPD symptoms for several days).

Who should not use ADVAIR DISKUS?

Do not use ADVAIR DISKUS if you:

- have a severe allergy to milk proteins. Ask your healthcare provider if you are not sure.
- are allergic to fluticasone propionate, salmeterol, or any of the ingredients in ADVAIR DISKUS. See “What are the ingredients in ADVAIR DISKUS?” below for a complete list of ingredients.

What should I tell my healthcare provider before using ADVAIR DISKUS?

Tell your healthcare provider about all of your health conditions, including if you:

- have heart problems.
- have high blood pressure.
- have seizures.
- have thyroid problems.
- have diabetes.
- have liver problems.
- have weak bones (osteoporosis).
- have an immune system problem.
- have eye problems such as glaucoma or cataracts.
- are allergic to any of the ingredients in ADVAIR DISKUS, any other medicines, or food products. See “What are the ingredients in ADVAIR DISKUS?” below for a complete list of ingredients.
- have any type of viral, bacterial, or fungal infection.
- are exposed to chickenpox or measles.
- have any other medical conditions.
- are pregnant or planning to become pregnant. It is not known if ADVAIR DISKUS may harm your unborn baby.
- are breastfeeding. It is not known if the medicines in ADVAIR DISKUS pass into your milk and if they can harm your baby.

Tell your healthcare provider about all the medicines you take, including prescription and over-the-counter medicines, vitamins, and herbal supplements. ADVAIR DISKUS and certain other medicines may interact with each other. This may cause serious side effects. Especially, tell your healthcare provider if you take antifungal or anti-HIV medicines.

Know the medicines you take. Keep a list of them to show your healthcare provider and pharmacist when you get a new medicine.

How should I use ADVAIR DISKUS?

Read the step-by-step instructions for using ADVAIR DISKUS at the end of this Medication Guide.

What should I avoid while using ADVAIR DISKUS?

- Do not use ADVAIR DISKUS unless your healthcare provider has taught you how to use the inhaler and you understand how to use it correctly.
- Children should use ADVAIR DISKUS with an adult’s help, as instructed by the child’s healthcare provider.
- ADVAIR DISKUS comes in 3 different strengths. Your healthcare provider prescribed the strength that is best for you.
- Use ADVAIR DISKUS exactly as your healthcare provider tells you to use it. Do not use ADVAIR DISKUS more often than prescribed.
- Use 1 inhalation of ADVAIR DISKUS 2 times each day. Use ADVAIR DISKUS at the same time each day, about 12 hours apart.
- If you miss a dose of ADVAIR DISKUS, just skip that dose. Take your next dose at your usual time. Do not take 2 doses at 1 time.
- If you take too much ADVAIR DISKUS, call your healthcare provider or go to the nearest hospital emergency room right away if you have any unusual symptoms, such as worsening shortness of breath, chest pain, increased heart rate, or shakiness.
- Do not use other medicines that contain a LABA for any reason. Ask your healthcare provider or pharmacist if any of your other medicines are LABA medicines.
- Do not stop using ADVAIR DISKUS unless told to do so by your healthcare provider because your symptoms might get worse. Your healthcare provider will change your medicines as needed.
- ADVAIR DISKUS does not relieve sudden breathing problems. Always have a rescue inhaler with you to treat sudden symptoms. If you do not have a rescue inhaler, call your healthcare provider to have one prescribed for you.
- Call your healthcare provider or get medical care right away if:
  - your breathing problems get worse.
  - you need to use your rescue inhaler more often than usual.
  - your rescue inhaler does not work as well to relieve your symptoms.
  - you need to use 4 or more inhalations of your rescue inhaler in 24 hours for 2 or more days in a row.
  - you use 1 whole canister of your rescue inhaler in 8 weeks.
  - your peak flow meter results decrease. Your healthcare provider will tell you the numbers that are right for you.
  - you have asthma and your symptoms do not improve after using ADVAIR DISKUS regularly for 1 week.

What are the possible side effects of ADVAIR DISKUS?

ADVAIR DISKUS can cause serious side effects, including:

- See “What is the most important information I should know about ADVAIR DISKUS?”
- fungal infection in your mouth or throat (thrush). Rinse your mouth with water without swallowing after using ADVAIR DISKUS to help reduce your chance of getting thrush.
- pneumonia. People with COPD have a higher chance of getting pneumonia. ADVAIR DISKUS may increase the chance of getting pneumonia. Call your healthcare provider if you notice any of the following symptoms:

• increase in mucus (sputum) production • chills

• change in mucus color • increased cough

• fever • increased breathing problems

- weakened immune system and increased chance of getting infections (immunosuppression).
- reduced adrenal function (adrenal insufficiency). Adrenal insufficiency is a condition where the adrenal glands do not make enough steroid hormones. This can happen when you stop taking oral corticosteroid medicines (such as prednisone) and start taking a medicine containing an inhaled steroid (such as ADVAIR DISKUS). During this transition period, when your body is under stress such as from fever, trauma (such as a car accident), infection, surgery, or worse COPD symptoms, adrenal insufficiency can get worse and may cause death.
- Symptoms of adrenal insufficiency include:

• feeling tired • nausea and vomiting

• lack of energy • low blood pressure

• weakness

- sudden breathing problems immediately after inhaling your medicine. If you have sudden breathing problems immediately after inhaling your medicine, stop using ADVAIR DISKUS and call your healthcare provider right away.
- serious allergic reactions. Call your healthcare provider or get emergency medical care if you get any of the following symptoms of a serious allergic reaction:

• rash • swelling of your face, mouth and tongue

• hives • breathing problems

- effects on heart.

• increased blood pressure • chest pain

• a fast or irregular heartbeat

- effects on nervous system.

• tremor • nervousness

- bone thinning or weakness (osteoporosis).
- slowed growth in children. A child’s growth should be checked often.
- eye problems including glaucoma and cataracts. You should have regular eye exams while using ADVAIR DISKUS.
- changes in laboratory blood levels (sugar, potassium, certain types of white blood cells)

Common side effects of ADVAIR DISKUS include:

Asthma:

• upper respiratory tract infection • bronchitis

• throat irritation • cough

• hoarseness and voice changes • headache

• thrush in your mouth or throat. Rinse your •nausea and vomiting

mouth with water without swallowing after
use to help prevent this.

In children with asthma, infections in the ear, nose, and throat are common.

COPD:

• thrush in your mouth or throat. Rinse your mouth with water •viral respiratory infections

without swallowing after use to help prevent this. •headache

• throat irritation •muscle and bone pain

• hoarseness and voice changes

Tell your healthcare provider about any side effect that bothers you or that does not go away.

These are not all the side effects with ADVAIR DISKUS. Ask your healthcare provider or pharmacist for more information.

Call your doctor for medical advice about side effects. You may report side effects to FDA at 1-800-FDA-1088.

How should I store ADVAIR DISKUS?

- Store ADVAIR DISKUS at room temperature between 68°F and 77°F (20°C and 25°C). Keep in a dry place away from heat and sunlight.
- Store ADVAIR DISKUS in the unopened foil pouch and only open when ready for use.
- Safely throw away ADVAIR DISKUS in the trash 1 month after you open the foil pouch or when the counter reads 0, whichever comes first.
- Keep ADVAIR DISKUS and all medicines out of the reach of children.

General information about the safe and effective use of ADVAIR DISKUS.

Medicines are sometimes prescribed for purposes not mentioned in a Medication Guide. Do not use ADVAIR DISKUS for a condition for which it was not prescribed. Do not give your ADVAIR DISKUS to other people, even if they have the same condition that you have. It may harm them.

This Medication Guide summarizes the most important information about ADVAIR DISKUS. If you would like more information, talk with your healthcare provider or pharmacist. You can ask your healthcare provider or pharmacist for information about ADVAIR DISKUS that was written for healthcare professionals.

What are the ingredients in ADVAIR DISKUS?

Active ingredients: fluticasone propionate, salmeterol xinafoate

Inactive ingredients: lactose monohydrate (contains milk proteins)

For more information about ADVAIR DISKUS, call 1-888-825-5249 or visit our website at www.advair.com.

ADVAIR DISKUS, DISKUS, and SEREVENT are registered trademarks of the GSK group of companies.

GlaxoSmithKline

Research Triangle Park, NC 27709

©2017 the GSK group of companies. All rights reserved.

ADD:10MG

1. This Medication Guide has been approved by the U.S. Food and Drug Administration. Revised: February 2017

INSTRUCTIONS FOR USE

ADVAIR DISKUS® [ ad′ vair disk′ us]

(fluticasone propionate and

salmeterol inhalation powder)

for oral inhalation

Read this Instructions for Use before you start using ADVAIR DISKUS and each time you get a refill. There may be new information. This information does not take the place of talking to your healthcare provider about your medical condition or treatment.

Your ADVAIR DISKUS inhaler

Figure A

Important information about your ADVAIR DISKUS inhaler:

- ADVAIR DISKUS is for oral inhalation use only.
- Take ADVAIR DISKUS out of the foil pouch just before you use it for the first time. Safely throw away the pouch. The DISKUS® will be in the closed position.
- Write the date you opened the foil pouch in the first blank line on the label. See Figure A.
- Write the “use by” date in the second blank line on the label. See Figure A. That date is 1 month after the date you wrote in the first line.
- The counter should read 60. If you have a sample (with “Sample” on the back label) or institutional (with “INSTITUTIONAL PACK” on the foil pouch) pack, the counter should read 14.

How to use your ADVAIR DISKUS inhaler

Follow these steps every time you use ADVAIR DISKUS.

Step 1. Open your ADVAIR DISKUS.

- Hold the DISKUS in your left hand and place the thumb of your right hand in the thumb grip. Push the thumb grip away from you as far as it will go until the mouthpiece shows and snaps into place. See Figure B.

Figure B

Step 2. Slide the lever until you hear it click.

Hold the DISKUS in a level, flat position with the mouthpiece towards you. Slide the lever away from the mouthpiece as far as it will go until it clicks. See Figure C.

Figure C

- The number on the counter will count down by 1. The DISKUS is now ready to use.

Follow the instructions below so you will not accidentally waste a dose:

- Do not close the DISKUS.
- Do not tilt the DISKUS.
- Do not move the lever on the DISKUS.

Step 3. Inhale your medicine.

- Before you breathe in your dose from the DISKUS, breathe out (exhale) as long as you can while you hold the DISKUS level and away from your mouth. See Figure D. Do not breathe into the mouthpiece.
- Put the mouthpiece to your lips. See Figure E. Breathe in quickly and deeply through the DISKUS. Do not breathe in through your nose.

Figure D

Figure E

- Remove the DISKUS from your mouth and hold your breath for about 10 seconds, or for as long as is comfortable for you.
- Breathe out slowly as long as you can. See Figure D.
- The DISKUS delivers your dose of medicine as a very fine powder that you may or may not taste or feel. Do not take an extra dose from the DISKUS even if you do not taste or feel the medicine.

Step 4. Close the DISKUS.

- Place your thumb in the thumb grip and slide it back towards you as far as it will go. See Figure F. Make sure the DISKUS clicks shut and you cannot see the mouthpiece.

Figure F

- The DISKUS is now ready for you to take your next scheduled dose in about 12 hours. When you are ready to take your next dose, repeat Steps 1 through 4.

Step 5. Rinse your mouth.

- Rinse your mouth with water after breathing in the medicine. Spit out the water. Do not swallow it. See Figure G.

Figure G

When should you get a refill?

The counter on top of the DISKUS shows you how many doses are left. After you have taken 55 doses (9 doses from the sample or institutional pack), the numbers 5 to 0 will show in red. See Figure H. These numbers warn you there are only a few doses left and are a reminder to get a refill.

Figure H

For correct use of the DISKUS, remember:

- Always use the DISKUS in a level, flat position.
- Make sure the lever firmly clicks into place.
- Hold your breath for about 10 seconds after inhaling. Then breathe out fully.
- After each dose, rinse your mouth with water and spit it out. Do not swallow the water.
- Do not take an extra dose, even if you did not taste or feel the powder.
- Do not take the DISKUS apart.
- Do not wash the DISKUS.
- Always keep the DISKUS in a dry place.
- Do not use the DISKUS with a spacer device.

If you have questions about ADVAIR DISKUS or how to use your inhaler, call GlaxoSmithKline (GSK) at 1-888-825-5249 or visit www.advair.com.

ADVAIR DISKUS and DISKUS are registered trademarks of the GSK group of companies.

GlaxoSmithKline

Research Triangle Park, NC 27709

©2017 the GSK group of companies. All rights reserved.

ADD:2IFU

1. This Instructions for Use has been approved by the U.S. Food and Drug Administration Revised: February 2017